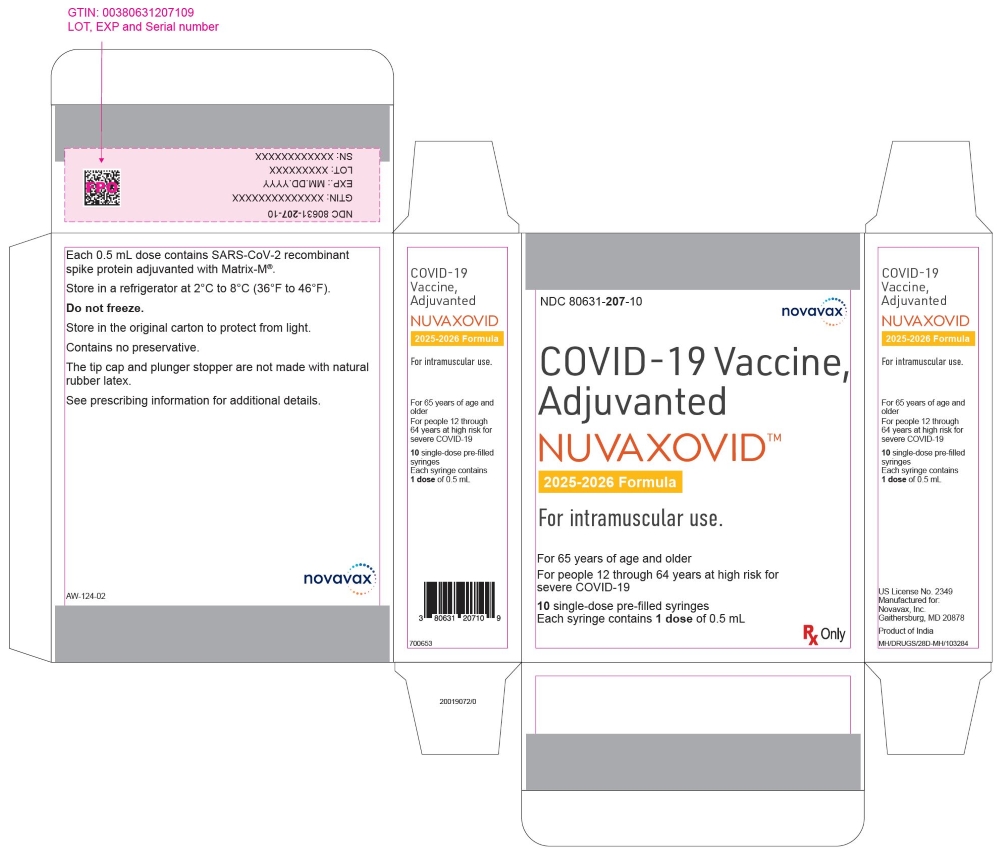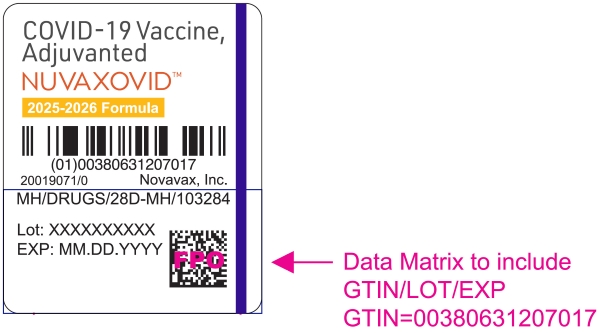 DRUG LABEL: NUVAXOVID COVID-19 Vaccine, Adjuvanted
NDC: 80631-200 | Form: INJECTION, SUSPENSION
Manufacturer: Novavax, Inc.
Category: other | Type: VACCINE LABEL
Date: 20250827

ACTIVE INGREDIENTS: NVX-COV2705 5 ug/0.5 mL
INACTIVE INGREDIENTS: CHOLESTEROL; EGG PHOSPHOLIPIDS; MONOBASIC POTASSIUM PHOSPHATE; POTASSIUM CHLORIDE; SODIUM PHOSPHATE, DIBASIC, DIHYDRATE; SODIUM PHOSPHATE, DIBASIC, HEPTAHYDRATE; SODIUM PHOSPHATE, MONOBASIC, MONOHYDRATE; SODIUM CHLORIDE; POLYSORBATE 80; SODIUM HYDROXIDE; HYDROCHLORIC ACID; WATER; MATRIX-M1 ADJUVANT

HIGHLIGHTS OF PRESCRIBING INFORMATION

These highlights do not include all the information needed to use NUVAXOVID safely and effectively. See full prescribing information for NUVAXOVID.
NUVAXOVIDTM (COVID-19 Vaccine, Adjuvanted) injectable suspension, for intramuscular use
2025-2026 Formula
Initial U.S. Approval: 2025

1 INDICATIONS AND USAGE

NUVAXOVID is a vaccine indicated for active immunization to prevent coronavirus disease 2019 (COVID-19) caused by severe acute respiratory syndrome coronavirus 2 (SARS-CoV-2).

NUVAXOVID is approved for use in individuals who are:

- 65 years of age and older, or
- 12 years through 64 years of age with at least one underlying condition that puts them at high risk for severe outcomes from COVID-19. (1)

2 DOSAGE AND ADMINISTRATION

- For intramuscular use. (2)
- Administer NUVAXOVID as a single 0.5 mL dose. (2.1)
- For individuals previously vaccinated with any COVID-19 vaccine, administer the dose of NUVAXOVID at least 2 months after the last dose of COVID-19 vaccine. (2.1)

3 DOSAGE FORMS AND STRENGTHS

NUVAXOVID is an injectable suspension. A single dose is 0.5 mL. (3)

4 CONTRAINDICATIONS

Do not administer NUVAXOVID to individuals with a known history of severe allergic reaction (e.g., anaphylaxis) to any component of NUVAXOVID or to individuals who had a severe allergic reaction (e.g., anaphylaxis) following a previous dose of a Novavax COVID-19 Vaccine, Adjuvanted. (4)

5 WARNINGS AND PRECAUTIONS

Clinical trials data provide evidence for increased risks of myocarditis and pericarditis following administration of NUVAXOVID. There have been postmarketing reports of myocarditis and pericarditis following administration of Novavax COVID-19 Vaccine, Adjuvanted. (5.2)

6 ADVERSE REACTIONS

The most commonly reported (> 10%) solicited adverse reactions after vaccination were:

- Participants 12 years through 17 years of age: injection site tenderness (up to 65.2%), injection site pain (up to 61%), headache (up to 56.9%), fatigue (up to 49.9%), muscle pain (up to 49.1%), malaise (up to 40.2%), nausea/vomiting (up to 19.9%), fever (up to 16.9%), and joint pain (up to 16.1%) (6.1)
- Participants 18 years through 64 years of age: injection site tenderness (up to 71.7%), injection site pain (up to 58.6%), muscle pain (up to 52.7%), fatigue (up to 50.5%), headache (up to 47.4%), malaise (up to 38.9%), joint pain (up to 22.2%), and nausea/vomiting (up to 12.1%) (6.1)
- Participants 65 years of age and older: injection site tenderness (up to 52.9%), injection site pain (up to 40.1%), fatigue (up to 29.2%), muscle pain (up to 29.2%), headache (up to 24.9%), malaise (up to 21.2%), and joint pain (up to 12.7%) (6.1)
- Participants 12 years through 17 years of age receiving a booster dose: injection site tenderness (65.9%), injection site pain (64.6%), headache (62.9%), muscle pain (60.4%), fatigue (57.1%), malaise (45.1%), nausea/vomiting (23.6%), joint pain (21.9%), fever (16.8%), and injection site redness (10.3%) (6.1)
- Participants 18 years of age and older receiving a booster dose: injection site tenderness (67.2%), injection site pain (56.4%), muscle pain (51.1%), fatigue (49.9%), headache (44.3%), malaise (37.7%), joint pain (24.2%), and nausea/vomiting (11.6%) (6.1)

To report SUSPECTED ADVERSE REACTIONS, contact Novavax, Inc. at 1-844-668-2829 or VAERS at 1-800-822-7967 or https://vaers.hhs.gov.

FULL PRESCRIBING INFORMATION

1 INDICATIONS AND USAGE

NUVAXOVID is a vaccine indicated for active immunization to prevent coronavirus disease 2019 (COVID-19) caused by severe acute respiratory syndrome coronavirus 2 (SARS-CoV-2).

NUVAXOVID is approved for use in individuals who are:

- 65 years of age and older, or
- 12 years through 64 years of age with at least one underlying condition that puts them at high risk for severe outcomes from COVID-19.

2 DOSAGE AND ADMINISTRATION

For intramuscular use.

2.1 Dose and Schedule

Administer NUVAXOVID as a single 0.5 mL dose.

For individuals previously vaccinated with any COVID-19 vaccine, administer the dose of NUVAXOVID at least 2 months after the last dose of COVID-19 vaccine.

2.2 Preparation for Administration

- Verify that the label on the pre-filled syringe states 2025-2026 Formula.
- NUVAXOVID is a colorless to slightly yellow, clear to mildly opalescent suspension.
- Parenteral drug products should be inspected visually for particulate matter and discoloration prior to administration, whenever solution and container permit. Do not administer the vaccine if either of these conditions exist.

2.3 Administration

Administer NUVAXOVID intramuscularly.

3 DOSAGE FORMS AND STRENGTHS

NUVAXOVID is an injectable suspension. A single dose is 0.5 mL.

4 CONTRAINDICATIONS

Do not administer NUVAXOVID to individuals with a known history of severe allergic reaction (e.g., anaphylaxis) to any component of NUVAXOVID [see Description (11)] or to individuals who had a severe allergic reaction (e.g., anaphylaxis) following a previous dose of Novavax COVID-19 Vaccine, Adjuvanted.

5 WARNINGS AND PRECAUTIONS

5.1 Management of Acute Allergic Reactions

Appropriate medical treatment must be immediately available to manage potential anaphylactic reactions following administration of NUVAXOVID.

5.2 Myocarditis and Pericarditis

Clinical trials data provide evidence for increased risks of myocarditis and pericarditis following administration of NUVAXOVID. There have been postmarketing reports of myocarditis and pericarditis following administration of Novavax COVID-19 Vaccine, Adjuvanted [see Adverse Reactions (6)].

The Centers for Disease Control and Prevention (CDC) has published considerations related to myocarditis and pericarditis after vaccination, including for vaccination of individuals with a history of myocarditis or pericarditis (https://www.cdc.gov/vaccines/covid-19/clinical-considerations/myocarditis.html).

5.3 Syncope

Syncope (fainting) may occur in association with administration of injectable vaccines, including NUVAXOVID. Procedures should be in place to avoid injury from fainting.

5.4 Altered Immunocompetence

Immunocompromised persons, including individuals receiving immunosuppressive therapy, may have a diminished immune response to NUVAXOVID [see Use in Specific Populations (8.6)].

5.5 Limitations of Vaccine Effectiveness

NUVAXOVID may not protect all vaccine recipients.

6 ADVERSE REACTIONS

An overview of clinical studies contributing to the safety assessment of NUVAXOVID in individuals 12 years of age and older is provided in Table 1. Participants in these clinical studies received a single dose, a 2-dose initial series (two doses 21 days apart; referred to as a primary series) and subsequent doses (referred to as booster doses) with Novavax COVID-19 Vaccine, Adjuvanted or with another COVID-19 vaccine manufactured by Novavax Inc.

Table 1: Clinical Studies
Study | Age | Vaccine Composition | Dosing Regimens | Vaccine Recipientsa
Study 1 (NCT04611802) | 18 years of age and older | Novavax COVID-19 Vaccine, Adjuvanted (Original monovalent)b | Primary Series | 26,106
Study 1 (NCT04611802) | 18 years of age and older | Novavax COVID-19 Vaccine, Adjuvanted (Original monovalent)b | 1st Booster | 13,353c,d
Study 1 (NCT04611802) | 12 years through 17 years of age | Novavax COVID-19 Vaccine, Adjuvanted (Original monovalent)b | Primary Series | 2,153
Study 1 (NCT04611802) | 12 years through 17 years of age | Novavax COVID-19 Vaccine, Adjuvanted (Original monovalent)b | 1st Booster | 1,499c
Study 2 (NCT04583995) | 18 years through 84 years of age | Novavax COVID-19 Vaccine, Adjuvanted (Original monovalent)b | Primary Series | 10,795
Study 3 (NCT04533399) | 18 years through 84 years of age | Novavax COVID-19 Vaccine, Adjuvanted (Original monovalent)b | Primary Series | 4,104
Study 3 (NCT04533399) | 18 years through 84 years of age | Novavax COVID-19 Vaccine, Adjuvanted (Original monovalent)b | 1st Booster | 1,898c
Study 4 (NCT04368988) | 18 years through 59 years of age (Part 1) | Novavax COVID-19 Vaccine, Adjuvanted (Original monovalent)b | Primary Series | 29
Study 4 (NCT04368988) | 18 years through 84 years of age (Part 2) | Novavax COVID-19 Vaccine, Adjuvanted (Original monovalent)b | Primary Series | 514
Study 4 (NCT04368988) | 18 years through 84 years of age (Part 2) | Novavax COVID-19 Vaccine, Adjuvanted (Original monovalent)b | 1st Booster | 105c
Study 4 (NCT04368988) | 18 years through 84 years of age (Part 2) | Novavax COVID-19 Vaccine, Adjuvanted (Original monovalent)b | 2nd Booster | 45c
Study 5 (NCT05463068) | 18 years through 49 years of age | Novavax COVID-19 Vaccine, Adjuvanted (Original monovalent)b | 1st or 2nd Booster | 905
Study 6 (NCT05372588) | 18 years through 64 years of age (Part 1) | Novavax COVID-19 Vaccine, Adjuvanted (Original monovalent)b | 2nd Booster | 274e
Study 6 (NCT05372588) | 18 years through 64 years of age (Part 1) | Monovalent Vaccine (Omicron BA.1)f | 2nd Booster | 286e
Study 6 (NCT05372588) | 18 years through 64 years of age (Part 1) | Bivalent Vaccine (Original monovalent and Omicron BA.1)g | 2nd Booster | 269e
Study 6 (NCT05372588) | 18 years of age and older (Part 2) | Novavax COVID-19 Vaccine, Adjuvanted (Original monovalent)b | 2nd Booster | 251e
Study 6 (NCT05372588) | 18 years of age and older (Part 2) | Monovalent Vaccine (Omicron BA.5)h | 2nd Booster | 254e
Study 6 (NCT05372588) | 18 years of age and older (Part 2) | Bivalent Vaccine (Original monovalent and Omicron BA.5)i | 2nd Booster | 259e
Study 7 (NCT05975060) | 18 years of age and older (Part 2) | Novavax COVID-19 Vaccine, Adjuvanted (2023-2024 Formula)j | Single Dose | 338
Abbreviation: SARS-CoV-2 = severe acute respiratory syndrome coronavirus 2.
a Receiving at least one dose of the intended dosing regimen.
b Vaccine containing a recombinant spike protein of SARS-CoV-2 Wuhan-Hu 1 strain (Original), authorized as Novavax COVID-19 Vaccine, Adjuvanted (Original monovalent).
c Booster dose recipients are a subset of the study population that received a primary series.
d Includes 43 participants who did not receive both primary series doses of Novavax COVID-19 Vaccine, Adjuvanted (Original monovalent) prior to receiving a dose of Novavax COVID-19 Vaccine, Adjuvanted (Original monovalent) in the booster vaccination period.
e Participants received at least 3 doses of an mRNA COVID-19 vaccine prior to inclusion in this study.
f Vaccine containing a recombinant spike protein of SARS-CoV-2 Omicron variant lineage BA.1, not authorized or approved in the U.S.
g Vaccine containing a recombinant spike protein of SARS-CoV-2 Wuhan-Hu 1 strain and Omicron variant lineage BA.1, not authorized or approved in the U.S.
h Vaccine containing a recombinant spike protein of SARS-CoV-2 Omicron variant lineage BA.5, not authorized or approved in the U.S.
i Vaccine containing a recombinant spike protein of SARS-CoV-2 Wuhan-Hu 1 strain and Omicron variant lineage BA.5, not authorized or approved in the U.S.
j Vaccine containing a recombinant spike protein of SARS-CoV-2 Omicron variant lineage XBB.1.5, authorized as Novavax COVID-19 Vaccine, Adjuvanted (2023-2024 Formula).

Safety data accrued in Studies 1, 5, 6, and 7 are relevant to NUVAXOVID because the vaccines administered in these studies were manufactured by the same manufacturing process as NUVAXOVID. Studies 2, 3 and 4, which utilized vaccines manufactured by a different process than NUVAXOVID, are considered supportive safety studies.

Adults 18 Years of Age and Older

2-Dose Series (Original Monovalent) in Vaccine-Naïve Adults

In participants 18 through 64 years of age, the most commonly reported (> 10%) solicited adverse reactions following administration of any dose of Novavax COVID-19 Vaccine, Adjuvanted (Original monovalent) were injection site tenderness (76.5%), injection site pain (64.3%), muscle pain (57.4%), fatigue (56.4%), headache (54.6%), malaise (43.2%), joint pain (25.1%), and nausea/vomiting (16.4%).

In participants 65 years of age and older, the most commonly reported (> 10%) solicited adverse reactions following administration of any dose of Novavax COVID-19 Vaccine, Adjuvanted (Original monovalent) were injection site tenderness (57.8%), injection site pain (44.1%), fatigue (36.3%), muscle pain (33.8%), headache (31.3%), malaise (24.3%), and joint pain (15.5%).

Single Dose (Original Monovalent) in Vaccine-Experienced Adults

In participants 18 through 64 years of age, the most commonly reported (> 10%) solicited adverse reactions following administration of a booster dose of Novavax COVID-19 Vaccine, Adjuvanted (Original monovalent) were injection site tenderness (69.4%), injection site pain (58.8%), muscle pain (54.3%), fatigue (52.5%), headache (47.3%), malaise (40.2%), joint pain (25.7%), and nausea/vomiting (12.5%).

In participants 65 years of age and older, the most commonly reported (> 10%) solicited adverse reactions following administration of a booster dose of Novavax COVID-19 Vaccine, Adjuvanted (Original monovalent) were injection site tenderness (54.4%), injection site pain (41.7%), muscle pain (32.1%), fatigue (34.2%), headache (26.1%), malaise (22.5%), and joint pain (14.9%).

Adolescents 12 Years of Age Through 17 Years of Age

2-Dose Series (Original Monovalent) in Vaccine-Naïve Adolescents

In participants 12 through 17 years of age, the most commonly reported (> 10%) solicited adverse reactions following administration of any dose of Novavax COVID-19 Vaccine, Adjuvanted (Original monovalent) were injection site tenderness (71.3%), injection site pain (67.1%), headache (63.3%), muscle pain (56.9%), fatigue (54.0%), malaise (43.0%), nausea/vomiting (23.1%), joint pain (19.4%), and fever (16.5%).

Single Dose (Original Monovalent) in Vaccine-Experienced Adolescents

In participants 12 through 17 years of age, the most commonly reported (> 10%) solicited adverse reactions following administration of a booster dose of Novavax COVID-19 Vaccine, Adjuvanted (Original monovalent) were injection site tenderness (65.9%), injection site pain (64.6%), headache (62.9%), muscle pain (60.4%), fatigue (57.1%), malaise (45.1%), nausea/vomiting (23.6%), joint pain (21.9%), fever (16.8%), and injection site redness (10.3%).

6.1 Clinical Trials Experience

Because clinical trials are conducted under widely varying conditions, adverse reaction rates observed in the clinical trials of a vaccine cannot be directly compared with rates in the clinical trials of another vaccine and may not reflect the rates observed in practice.

Adults 18 Years of Age and Older

2-Dose Series (Original Monovalent) in Vaccine-Naïve Adults

Safety of Novavax COVID-19 Vaccine, Adjuvanted (Original monovalent) was assessed in a clinical study conducted in the United States (US) and Mexico (NCT04611802; Study 1). In this study, 26,106 participants 18 years of age and older received at least one primary series dose of Novavax COVID-19 Vaccine, Adjuvanted (Original monovalent). Additional supportive safety data are available from three other clinical trials in the United Kingdom (NCT04583995; Study 2), South Africa (NCT04533399; Study 3), and Australia (NCT04368988, Part 1 and Part 2 in Australia and the US; Study 4) which evaluated a COVID-19 vaccine containing the SARS-CoV-2 recombinant spike (rS) protein and Matrix-M® adjuvant but manufactured by a different process than Novavax COVID-19 Vaccine, Adjuvanted (Original monovalent).

Study 1 was a Phase 3, multicenter, randomized (2:1), observer-blinded, placebo-controlled, crossover study in adult participants 18 years of age and older in the US and Mexico. Participants were randomized (2:1) to receive 2 doses of the vaccine or placebo administered 21 days apart.

In the adult part of Study 1, participants received Novavax COVID-19 Vaccine, Adjuvanted (Original monovalent) (n=19,735) or placebo (n=9,847) in the pre-crossover period. In the pre-crossover period, among participants who received at least one dose of vaccine, 52.5% were male, 47.5% were female; 75.0% were White, 11.8% were Black or African American, 4.1% were Asian, 6.6% were American Indian (including Native Americans) or Alaskan Native, and 1.7% were multiple races; 22.0% were Hispanic/Latino. Demographic characteristics of participants were similar between the Novavax COVID-19 Vaccine, Adjuvanted (Original monovalent) and placebo groups. During the study, COVID-19 vaccines authorized for emergency use became available, and participants, when eligible for vaccination, were offered the opportunity to cross over from the originally assigned study treatment to the other study treatment (vaccine or placebo) in a blinded fashion (“blinded crossover”). Due to data quality issues at two study sites, a total of 289 participants were excluded from the safety analysis set. In the post-crossover period, 6,416 participants who had initially received placebo and subsequently received Novavax COVID-19 Vaccine, Adjuvanted (Original monovalent) [referred to as Placebo/Novavax COVID-19 Vaccine, Adjuvanted (Original monovalent)]; and 15,298 participants who had initially received Novavax COVID-19 Vaccine, Adjuvanted (Original monovalent) and subsequently received placebo [referred to as Novavax COVID-19 Vaccine, Adjuvanted (Original monovalent)/Placebo]. The demographic characteristics were similar between participants in the pre-crossover and post-crossover groups.

Solicited Adverse Reactions

During the pre-crossover period, local and systemic adverse reactions were solicited within 7 days following each dose of Novavax COVID-19 Vaccine, Adjuvanted (Original monovalent) or placebo in participants using an electronic diary.

The reported frequency and severity of solicited local and systemic adverse reactions in participants 18 through 64 years of age are presented in Table 2.

Table 2: Number and Percentage of Participants with Soliciteda Local and Systemic Adverse Reactions Starting Within 7 Daysb After Each Dose of the Primary Series in Participants 18 through 64 Years of Age, Study 1 (Solicited Safety Set, Dose 1 and Dose 2)c
Event | Novavax COVID-19 Vaccine, Adjuvanted (Original Monovalent) |  | Placebod
Event | Dose 1 N=16,041 n (%) | Dose 2 N=16,106 n (%) | Dose 1 N=7,968 n (%) | Dose 2 N=7,859 n (%)
Local Adverse Reactionse
Tendernessf
Any Grade | 8,796 (54.8) | 11,543 (71.7) | 1,379 (17.3) | 1,221 (15.5)
Grade 3 | 146 (0.9) | 811 (5.0) | 16 (0.2) | 17 (0.2)
Grade 4 | 0 | 2 (< 0.1) | 0 | 0
Paing
Any Grade | 5,816 (36.3) | 9,436 (58.6) | 921 (11.6) | 1,041 (13.2)
Grade 3 | 52 (0.3) | 287 (1.8) | 2 (< 0.1) | 6 (< 0.1)
Grade 4 | 0 | 1 (< 0.1) | 0 | 0
Redness (erythema)h
Any Grade | 148 (0.9) | 1,039 (6.5) | 23 (0.3) | 26 (0.3)
Grade 3 | 2 (< 0.1) | 119 (0.7) | 0 | 2 (< 0.1)
Swellingi
Any Grade | 136 (0.8) | 945 (5.9) | 23 (0.3) | 22 (0.3)
Grade 3 | 4 (< 0.1) | 67 (0.4) | 1 (< 0.1) | 1 (< 0.1)
Systemic Adverse Reactionse
Fatiguej
Any Grade | 4,343 (27.1) | 8,133 (50.5) | 1,894 (23.8) | 1,723 (21.9)
Grade 3 | 391 (2.4) | 2,522 (15.7) | 190 (2.4) | 307 (3.9)
Grade 4 | 3 (< 0.1) | 2 (< 0.1) | 1 (< 0.1) | 3 (< 0.1)
Headachek
Any Grade | 4,292 (26.8) | 7,630 (47.4) | 1,942 (24.4) | 1,596 (20.3)
Grade 3 | 134 (0.8) | 500 (3.1) | 58 (0.7) | 36 (0.5)
Grade 4 | 4 (< 0.1) | 2 (< 0.1) | 1 (< 0.1) | 2 (< 0.1)
Muscle pain (myalgia)j
Any Grade | 3,949 (24.6) | 8,490 (52.7) | 1,142 (14.3) | 1,010 (12.9)
Grade 3 | 79 (0.5) | 818 (5.1) | 31 (0.4) | 28 (0.4)
Grade 4 | 2 (< 0.1) | 2 (< 0.1) | 1 (< 0.1) | 4 (< 0.1)
Malaisej
Any Grade | 2,460 (15.3) | 6,273 (38.9) | 963 (12.1) | 943 (12.0)
Grade 3 | 126 (0.8) | 1,043 (6.5) | 52 (0.7) | 54 (0.7)
Grade 4 | 6 (< 0.1) | 5 (< 0.1) | 1 (< 0.1) | 2 (< 0.1)
Joint pain (arthralgia)j
Any Grade | 1,272 (7.9) | 3,574 (22.2) | 528 (6.6) | 514 (6.5)
Grade 3 | 49 (0.3) | 403 (2.5) | 25 (0.3) | 22 (0.3)
Grade 4 | 1 (< 0.1) | 2 (< 0.1) | 0 | 2 (< 0.1)
Nausea or vomitingl
Any Grade | 1,150 (7.2) | 1,953 (12.1) | 513 (6.4) | 443 (5.6)
Grade 3 | 18 (0.1) | 29 (0.2) | 7 (< 0.1) | 7 (< 0.1)
Grade 4 | 4 (< 0.1) | 5 (< 0.1) | 2 (< 0.1) | 2 (< 0.1)
Feverm
Any Grade | 61 (0.4) | 1,062 (6.6) | 31 (0.4) | 22 (0.3)
Grade 3 | 8 (< 0.1) | 79 (0.5) | 7 (< 0.1) | 5 (< 0.1)
Grade 4 | 7 (< 0.1) | 2 (< 0.1) | 1 (< 0.1) | 2 (< 0.1)
a Solicited reactogenicity events and use of antipyretic or pain medication were collected by the participant in the electronic diary (eDiary).
b 7 days included day of vaccination and the subsequent 6 days.
c The analysis included 16,041 (Dose 1) and 16,106 (Dose 2) participants in the Novavax COVID-19 Vaccine, Adjuvanted (Original monovalent) group and 7,968 (Dose 1) and 7,859 (Dose 2) participants in the placebo group who received at least one dose and completed at least one day of the vaccination reactogenicity diary, reported an unsolicited adverse event that was mapped to a reactogenicity term within 7 days of the dose, reported a symptom in the Daily Illness Symptoms Diary that was mapped to a reactogenicity term within 7 days of the dose, or reported a temperature in the Daily Illness Symptoms Diary within 7 days of the dose.
d Placebo was a saline solution.
e Absence of rows for Grade 4 adverse reactions indicates no events were reported.
f Any Grade = any event that is ≥ Grade 1, where Grade 1 = Mild discomfort to touch; Grade 2 = Discomfort with movement; Grade 3 = Significant discomfort at rest; Grade 4 = Emergency room (ER) visit or hospitalization.
g Any Grade = any event that is ≥ Grade 1, where Grade 1 = Does not interfere with activity; Grade 2 = Repeated use of non-narcotic pain reliever > 24 hours or interferes with activity; Grade 3 = Any use of narcotic pain reliever or prevents daily activity; Grade 4 = ER visit or hospitalization.
h Any Grade = any event that is ≥ Grade 1, where Grade 1 = 2.5 – 5 cm; Grade 2 = 5.1 – 10 cm; Grade 3 = > 10 cm; Grade 4 = Necrosis or exfoliative dermatitis.
i Any Grade = any event that is ≥ Grade 1, where Grade 1 = 2.5 – 5 cm and does not interfere with activity; Grade 2 = 5.1 – 10 cm or interferes with activity; Grade 3 = > 10 cm or prevents daily activity; Grade 4 = Necrosis.
j Any Grade = any event that is ≥ Grade 1, where Grade 1 = No interference with activity; Grade 2 = Some interference with activity; Grade 3 = Significant; prevents daily activity; Grade 4 = ER visit or hospitalization.
k Any Grade = any event that is ≥ Grade 1, where Grade 1 = No interference with activity; Grade 2 = Repeated use of non-narcotic pain reliever > 24 hours or some interference with activity; Grade 3 = Significant; any use of narcotic pain reliever or prevents daily activity; Grade 4 = ER visit or hospitalization.
l Any Grade = any event that is ≥ Grade 1, where Grade 1 = No interference with activity or 1 – 2 episodes/24 hours; Grade 2 = Some interference with activity or > 2 episodes/24 hours; Grade 3 = Prevents daily activity, requires outpatient IV hydration; Grade 4 = ER visit or hospitalization for hypotensive shock.
m Any Grade = any event that is ≥ Grade 1, where Grade 1 = 38.0 – 38.4°C (100.4 – 101.1°F); Grade 2 = 38.5 – 38.9°C (101.2 – 102.0°F); Grade 3 = 39.0 – 40°C (102.1 – 104°F); Grade 4 = > 40°C (> 104°F).

The reported frequency and severity of solicited local and systemic adverse reactions are presented for participants 65 years of age and older in Table 3.

Table 3: Number and Percentage of Participants with Soliciteda Local and Systemic Adverse Reactions Starting Within 7 Daysb After Each Dose of the Primary Series in Participants 65 Years of Age and Older, Study 1 (Solicited Safety Set, Dose 1 and Dose 2)c
Event | Novavax COVID-19 Vaccine, Adjuvanted (Original Monovalent) |  | Placebod
Event | Dose 1 N=2,293 n (%) | Dose 2 N=2,217 n (%) | Dose 1 N=1,138 n (%) | Dose 2 N=1,057 n (%)
Local Adverse Reactionse
Tendernessf
Any Grade | 772 (33.7) | 1,173 (52.9) | 148 (13.0) | 108 (10.2)
Grade 3 | 10 (0.4) | 33 (1.5) | 2 (0.2) | 1 (< 0.1)
Paing
Any Grade | 461 (20.1) | 890 (40.1) | 93 (8.2) | 114 (10.8)
Grade 3 | 3 (0.1) | 14 (0.6) | 1 (< 0.1) | 1 (< 0.1)
Redness (erythema)h
Any Grade | 17 (0.7) | 103 (4.6) | 5 (0.4) | 4 (0.4)
Grade 3 | 0 | 7 (0.3) | 0 | 0
Swellingi
Any Grade | 17 (0.7) | 116 (5.2) | 2 (0.2) | 4 (0.4)
Grade 3 | 0 | 5 (0.2) | 0 | 0
Systemic Adverse Reactionse
Fatiguej
Any Grade | 431 (18.8) | 647 (29.2) | 196 (17.2) | 163 (15.4)
Grade 3 | 73 (3.2) | 138 (6.2) | 27 (2.4) | 34 (3.2)
Headachek
Any Grade | 382 (16.7) | 551 (24.9) | 199 (17.5) | 161 (15.2)
Grade 3 | 12 (0.5) | 18 (0.8) | 4 (0.4) | 2 (0.2)
Grade 4 | 0 | 1 (< 0.1) | 0 | 0
Muscle pain (myalgia)j
Any Grade | 324 (14.1) | 648 (29.2) | 144 (12.7) | 115 (10.9)
Grade 3 | 3 (0.1) | 32 (1.4) | 4 (0.4) | 2 (0.2)
Malaisej
Any Grade | 230 (10.0) | 469 (21.2) | 100 (8.8) | 95 (9.0)
Grade 3 | 12 (0.5) | 40 (1.8) | 4 (0.4) | 5 (0.5)
Joint pain (arthralgia)j
Any Grade | 141 (6.1) | 282 (12.7) | 72 (6.3) | 63 (6.0)
Grade 3 | 4 (0.2) | 16 (0.7) | 4 (0.4) | 2 (0.2)
Nausea/vomitingl
Any Grade | 120 (5.2) | 132 (6.0) | 47 (4.1) | 39 (3.7)
Grade 3 | 0 | 2 (< 0.1) | 0 | 0
Feverm
Any Grade | 9 (0.4) | 45 (2.0) | 6 (0.5) | 7 (0.7)
Grade 3 | 1 (< 0.1) | 2 (< 0.1) | 0 | 1 (< 0.1)
Grade 4 | 0 | 0 | 2 (0.2) | 0
a Solicited reactogenicity events and use of antipyretic or pain medication were collected by the participant in the electronic diary (eDiary).
b 7 days included day of vaccination and the subsequent 6 days.
c The analysis included 2,293 (Dose 1) and 2,217 (Dose 2) participants in the Novavax COVID-19 Vaccine, Adjuvanted (Original monovalent) group and 1,138 (Dose 1) and 1,057 (Dose 2) participants in the placebo group who received at least one dose and completed at least one day of the vaccination reactogenicity diary, reported an unsolicited adverse event that was mapped to a reactogenicity term within 7 days of the dose, reported a symptom in the Daily Illness Symptoms Diary that was mapped to a reactogenicity term within 7 days of the dose, or reported a temperature in the Daily Illness Symptoms Diary within 7 days of the dose.
d Placebo was a saline solution.
e Absence of rows for Grade 4 adverse reactions indicates no events were reported.
f Any Grade = any event that is ≥ Grade 1, where Grade 1 = Mild discomfort to touch; Grade 2 = Discomfort with movement; Grade 3 = Significant discomfort at rest; Grade 4 = Emergency room (ER) visit or hospitalization.
g Any Grade = any event that is ≥ Grade 1, where Grade 1 = Does not interfere with activity; Grade 2 = Repeated use of non-narcotic pain reliever > 24 hours or interferes with activity; Grade 3 = Any use of narcotic pain reliever or prevents daily activity; Grade 4 = ER visit or hospitalization.
h Any Grade = any event that is ≥ Grade 1, where Grade 1 = 2.5 – 5 cm; Grade 2 = 5.1 – 10 cm; Grade 3 = > 10 cm; Grade 4 = Necrosis or exfoliative dermatitis.
i Any Grade = any event that is ≥ Grade 1, where Grade 1 = 2.5 – 5 cm and does not interfere with activity; Grade 2 = 5.1 – 10 cm or interferes with activity; Grade 3 = > 10 cm or prevents daily activity; Grade 4 = Necrosis.
j Any Grade = any event that is ≥ Grade 1, where Grade 1 = No interference with activity; Grade 2 = Some interference with activity; Grade 3 = Significant; prevents daily activity; Grade 4 = ER visit or hospitalization.
k Any Grade = any event that is ≥ Grade 1, where Grade 1 = No interference with activity; Grade 2 = Repeated use of non-narcotic pain reliever > 24 hours or some interference with activity; Grade 3 = Significant; any use of narcotic pain reliever or prevents daily activity; Grade 4 = ER visit or hospitalization.
l Any Grade = any event that is ≥ Grade 1, where Grade 1 = No interference with activity or 1 – 2 episodes/24 hours; Grade 2 = Some interference with activity or > 2 episodes/24 hours; Grade 3 = Prevents daily activity, requires outpatient IV hydration; Grade 4 = ER visit or hospitalization for hypotensive shock.
m Any Grade = any event that is ≥ Grade 1, where Grade 1 = 38.0 – 38.4°C (100.4 – 101.1°F); Grade 2 = 38.5 – 38.9°C (101.2 – 102.0°F); Grade 3 = 39.0 – 40°C (102.1 – 104°F); Grade 4 = > 40°C (> 104°F).

Unsolicited Adverse Events

In Study 1, participants were monitored for unsolicited adverse events from the first dose through 28 days after the second dose in both the pre- and post-crossover periods. Serious adverse events, adverse events of special interest (AESI) and vaccine-related medically attended adverse events were recorded for the entirety of study participation. Participants who received at least one dose in the pre- or post-crossover periods were included in the safety analysis. In the pre-crossover period 19,735 participants received Novavax COVID-19 Vaccine, Adjuvanted (Original monovalent) and 9,847 participants received placebo. In the post-crossover period, 6,416 participants received Novavax COVID-19 Vaccine, Adjuvanted (Original monovalent) and 15,298 received placebo. Of participants who received two doses of Novavax COVID-19 Vaccine, Adjuvanted (Original monovalent) in the pre-crossover period (n=19,075), 76% had a follow-up duration of at least 2 months (median = 2.5 months) after Dose 2. Of participants who received two doses of Novavax COVID-19 Vaccine, Adjuvanted (Original monovalent) in the post-crossover period (n=6,306), 98% had a follow-up duration of at least 2 months (median = 8.3 months) after the last dose.

From Dose 1 through 28 days following Dose 2 in the pre-crossover period, the overall frequency of unsolicited adverse events was similar in the Novavax COVID-19 Vaccine, Adjuvanted (Original monovalent) group (11.8%) and the placebo group (11.0%). Unsolicited adverse events reported following any dose, through 28 days following Dose 2, not already captured by solicited local and systemic reactions, in the Novavax COVID-19 Vaccine, Adjuvanted (Original monovalent) group and placebo group included chills (0.3% vs < 0.1% pre-crossover and < 0.1% vs < 0.1% post-crossover), lymphadenopathy (0.2% vs 0.1% pre-crossover and 0.1% vs < 0.1% post-crossover) and injection site pruritus (0.1% vs 0.0% pre-crossover and 0.1% vs 0.0% post-crossover), respectively.

In the pre-crossover period, serious adverse events were reported by 228 (1.2%) participants in the Novavax COVID-19 Vaccine, Adjuvanted (Original monovalent) group and by 115 (1.2%) participants in the placebo group. In the post-crossover period, serious adverse events were reported by 164 (2.6%) participants who received Placebo/Novavax COVID-19 Vaccine, Adjuvanted (Original monovalent) and by 364 (2.4%) participants who received Novavax COVID-19 Vaccine, Adjuvanted (Original monovalent)/Placebo.

Within 7 days of any dose (including 26,106 Novavax COVID-19 Vaccine, Adjuvanted (Original monovalent) recipients and 25,145 placebo recipients, of which 15,298 received Novavax COVID-19 Vaccine, Adjuvanted (Original monovalent) in the pre-crossover period, in both the pre- and post-crossover periods), hypersensitivity reactions (including urticaria, hypersensitivity, angioedema, and swelling of the face, lips, periorbital, and/or eyelids) were reported by 30 (0.11%) participants after Novavax COVID-19 Vaccine, Adjuvanted (Original monovalent) and 9 (0.04%) participants after placebo. Of these events, 1 reaction (generalized urticaria and facial angioedema with a duration of 2 days) was serious and occurred 2 days after Dose 1 of Novavax COVID-19 Vaccine, Adjuvanted (Original monovalent).

In Study 1, myocarditis and/or pericarditis were reported. A total of 3 events of myocarditis and/or pericarditis were reported by 2 (0.01%) participants after the Novavax COVID-19 Vaccine, Adjuvanted (Original monovalent) and a total of 2 events were reported in 2 participants (0.01%) after placebo (one of whom had received Novavax COVID-19 Vaccine, Adjuvanted [Original monovalent] 504 days prior to the event during the pre-crossover period). After Novavax COVID-19 Vaccine, Adjuvanted, one serious event was reported by a 67-year-old male 28 days after Dose 1, associated with concomitant COVID-19, and non-serious events of myocarditis and pericarditis (n=1 each) were reported by a 20-year-old male 10 days after Dose 1. Among the three reported events, one was reported as resolved and two did not have follow-up available. Reports of myocarditis and/or pericarditis from Study 1 and Study 2 (see Safety Data from Study 2) provide evidence for increased risks of myocarditis and pericarditis following administration of the Novavax COVID-19 Vaccine, Adjuvanted.

In the pre-crossover period of Study 1, atrial fibrillation was reported in 13 (0.07%) participants who received Novavax COVID-19 Vaccine, Adjuvanted (Original monovalent), and 4 (0.04%) participants who received placebo (of which 10 (0.05%) participants in the Novavax COVID-19 Vaccine, Adjuvanted (Original monovalent) arm and 2 (0.02%) participants in the placebo arm experienced events that were serious). Of the total cases reported in the pre-crossover period, onset of atrial fibrillation within 30 days post vaccination occurred in 6 (0.03%) participants compared with 2 (0.02%) participants in the placebo group [of which 3 (0.02%) participants in the Novavax COVID-19 Vaccine, Adjuvanted (Original monovalent) arm and 0 participants in the placebo arm experienced events that were serious]. The currently available information on atrial fibrillation is insufficient to determine a causal relationship to the vaccine.

Within 28 days of any dose, the following numerical imbalances with more events in vaccine than placebo recipients [including 26,106 Novavax COVID-19 Vaccine, Adjuvanted (Original monovalent) recipients and 25,145 placebo recipients in both the pre- and post-crossover periods] were observed for the following serious and other adverse events of interest:

Within 28 days after vaccination throughout the study duration including after booster dose, events of cardiomyopathy, cardiac failure, congestive cardiomyopathy, congestive cardiac failure, acute cardiac failure, left ventricular failure, or acute left ventricular failure were reported. Ten events were reported by 10 (0.04%) participants after Novavax COVID-19 Vaccine, Adjuvanted (Original monovalent) was administered as a primary series (6 events) or booster dose (4 events), and 3 events were reported in 2 (0.01%) participants after placebo (one of whom had received Novavax COVID-19 Vaccine, Adjuvanted [Original monovalent] during the pre-crossover period). All events were serious except congestive cardiac failure (n=2), cardiomyopathy (n=2) and congestive cardiomyopathy (n=1) after Novavax COVID-19 Vaccine, Adjuvanted (Original monovalent). Currently available information on cardiomyopathy or cardiac failure is insufficient to determine a causal relationship with the vaccine.

Within 28 days after vaccination in the pre- or post-crossover period, a total of 6 events of acute cholecystitis or cholecystitis were reported by 6 (0.02%) participants after Novavax COVID-19 Vaccine, Adjuvanted (Original monovalent) and a total of 2 events were reported by 2 (0.01%) participants after placebo (both of whom had received Novavax COVID-19 Vaccine, Adjuvanted [Original monovalent] during the pre-crossover period). All events were serious. Currently available information on acute cholecystitis or cholecystitis is insufficient to determine a causal relationship with the vaccine.

Within 28 days after vaccination in the pre- or post-crossover period, a total of 12 non-cardiac, non-neurovascular thrombotic and embolic events were reported by 11 (0.04%) participants after the Novavax COVID-19 Vaccine, Adjuvanted (Original monovalent) and a total of 7 events were reported by 6 (0.02%) participants after placebo (five of whom had received Novavax COVID-19 Vaccine, Adjuvanted [Original monovalent] during the pre-crossover period). Events following the Novavax COVID-19 Vaccine, Adjuvanted (Original monovalent) included pulmonary embolism (n=5), deep vein thrombosis (n=2), thrombosis (n=2), mesenteric artery thrombosis, peripheral arterial occlusive disease and portal vein thrombosis (n=1 each); six events were serious, including pulmonary embolism (n=5) and deep vein thrombosis (n=1). Events following placebo included pulmonary embolism (n=3), and deep vein thrombosis and peripheral arterial occlusive disease (n=2 each), all of which were serious except deep vein thrombosis and peripheral arterial occlusive disease (n=1 each). Currently available information on non-cardiac, non-neurovascular thrombotic and embolic events is insufficient to determine a causal relationship with the vaccine.

A total of 5 events of iridocyclitis, iritis or uveitis were reported by 3 (0.01%) participants after Novavax COVID-19 Vaccine, Adjuvanted (Original monovalent) and a total of 2 events were reported by 2 (0.01%) participants after placebo. All events were non-serious. One participant had onset of uveitis after Dose 1 of Novavax COVID-19 Vaccine, Adjuvanted (Original monovalent) which resolved and then recurred following Dose 2. The two placebo recipients with events appeared to have had a previous history of uveitis and one of the Novavax COVID-19 Vaccine, Adjuvanted (Original monovalent) recipients had a history of iritis. Currently available information on iridocyclitis, iritis or uveitis is insufficient to determine a causal relationship with the vaccine.

Single Dose (Original Monovalent) in Vaccine-Experienced Adults

In an open-label portion of Study 1, 13,310 participants 18 years of age and older received a single booster dose of Novavax COVID-19 Vaccine, Adjuvanted (Original monovalent) (0.5 mL) at least 6 months after the two-dose primary series (median of 11.0 months between completion of primary series and booster dose); an additional 43 participants received the booster dose after receiving only one dose in the two-dose primary series. Safety analyses included evaluation of solicited local and systemic adverse reactions within 7 days after a booster dose for participants who completed the electronic diary (n=11,447) and unsolicited adverse events within 28 days after a booster dose (n=13,353). Safety analyses also included evaluation of serious adverse events and adverse events of special interest after a booster dose (n=13,353) with a median follow-up of 6.7 months (0 – 8 months).

Among the 13,353 boosted participants, 84.5% were between 18 and 64 years of age and 15.5% were 65 years of age and older, 50.6% were male, 49.4% were female; 71.8% were White, 14.1% were Black or African American, 3.7% were Asian, 7.8% were American Indian (including Native Americans) or Alaskan Native, 0.2% were Native Hawaiian or Other Pacific Islander, and 1.7% were multiple races; 23.4% were Hispanic or Latino.

Solicited Adverse Reactions

Local and systemic adverse reactions were solicited within 7 days following the booster dose of Novavax COVID-19 Vaccine, Adjuvanted (Original monovalent) using an electronic diary.

The reported frequency and severity of solicited local and systemic adverse reactions in participants 18 years of age and older are presented in Table 4.

Table 4: Number and Percentage of Participants with Soliciteda Local and Systemic Adverse Reactions Starting within 7 Daysb After Booster Dose in Participants 18 through 64 Years and 65 Years of Age and Older, Study 1 (Booster Safety Analysis Set)c
Event | Novavax COVID-19 Vaccine, Adjuvanted (Original Monovalent); Booster
Event | Participants 18 through 64 Years N=9,817 n (%) | Participants 65 Years and Older N=1,630 n (%)
Local Adverse Reactionsd
Tendernesse
Any Grade | 6811 (69.4) | 887 (54.4)
Grade 3 | 676 (6.9) | 35 (2.1)
Grade 4 | 6 (< 0.1) | 1 (< 0.1)
Painf
Any Grade | 5773 (58.8) | 680 (41.7)
Grade 3 | 295 (3.0) | 18 (1.1)
Grade 4 | 4 (< 0.1) | 2 (0.1)
Redness (erythema)g
Any Grade | 843 (8.6) | 110 (6.7)
Grade 3 | 170 (1.7) | 13 (0.8)
Swellingh
Any Grade | 765 (7.8) | 108 (6.6)
Grade 3 | 101 (1.0) | 8 (0.5)
Systemic Adverse Reactionsd
Muscle pain (myalgia)i
Any Grade | 5,329 (54.3) | 523 (32.1)
Grade 3 | 853 (8.7) | 40 (2.5)
Grade 4 | 10 (0.1) | 1 (< 0.1)
Fatiguei
Any Grade | 5,150 (52.5) | 558 (34.2)
Grade 3 | 1839 (18.7) | 130 (8.0)
Grade 4 | 12 (0.1) | 0
Headachej
Any Grade | 4,645 (47.3) | 426 (26.1)
Grade 3 | 539 (5.5) | 30 (1.8)
Grade 4 | 6 (< 0.1) | 0
Malaisei
Any Grade | 3,946 (40.2) | 366 (22.5)
Grade 3 | 935 (9.5) | 50 (3.1)
Grade 4 | 12 (0.1) | 0
Joint pain (arthralgia)i
Any Grade | 2,525 (25.7) | 243 (14.9)
Grade 3 | 495 (5.0) | 27 (1.7)
Grade 4 | 5 (< 0.1) | 1 (< 0.1)
Nausea or vomitingk
Any Grade | 1,232 (12.5) | 98 (6.0)
Grade 3 | 45 (0.5) | 2 (0.1)
Grade 4 | 5 (< 0.1) | 0
Feverl
Any Grade | 860 (8.8) | 69 (4.2)
Grade 3 | 121 (1.2) | 5 (0.3)
Grade 4 | 5 (< 0.1) | 1 (< 0.1)
a Solicited reactogenicity events and use of antipyretic or pain medication were collected by the participant in the electronic diary (eDiary).
b 7 days included day of vaccination and the subsequent 6 days.
c The analysis included 9,817 participants 18 through 64 years and 1,630 participants ≥ 65 years who received the booster dose and completed at least one day of the vaccination reactogenicity diary, reported an unsolicited adverse event that was mapped to a reactogenicity term within 7 days of the dose, reported a symptom in the Daily Illness Symptoms Diary that was mapped to a reactogenicity term within 7 days of the dose, or reported a temperature in the Daily Illness Symptoms Diary within 7 days of the dose.
d Absence of rows for Grade 4 adverse reactions indicates no events were reported.
e Any Grade = any event that is ≥ Grade 1, where Grade 1 = Mild discomfort to touch; Grade 2 = Discomfort with movement; Grade 3 = Significant discomfort at rest; Grade 4 = Emergency room (ER) visit or hospitalization.
f Any Grade = any event that is ≥ Grade 1, where Grade 1 = Does not interfere with activity; Grade 2 = Repeated use of non-narcotic pain reliever > 24 hours or interferes with activity; Grade 3 = Any use of narcotic pain reliever or prevents daily activity; Grade 4 = ER visit or hospitalization.
g Any Grade = any event that is ≥ Grade 1, where Grade 1 = 2.5 – 5 cm; Grade 2 = 5.1 – 10 cm; Grade 3 = > 10 cm; Grade 4 = Necrosis or exfoliative dermatitis.
h Any Grade = any event that is ≥ Grade 1, where Grade 1 = 2.5 – 5 cm and does not interfere with activity; Grade 2 = 5.1 – 10 cm or interferes with activity; Grade 3 = > 10 cm or prevents daily activity; Grade 4 = Necrosis.
i Any Grade = any event that is ≥ Grade 1, where Grade 1 = No interference with activity; Grade 2 = Some interference with activity; Grade 3 = Significant; prevents daily activity; Grade 4 = ER visit or hospitalization.
j Any Grade = any event that is ≥ Grade 1, where Grade 1 = No interference with activity; Grade 2 = Repeated use of non-narcotic pain reliever > 24 hours or some interference with activity; Grade 3 = Significant; any use of narcotic pain reliever or prevents daily activity; Grade 4 = ER visit or hospitalization.
k Any Grade = any event that is ≥ Grade 1, where Grade 1 = No interference with activity or 1 – 2 episodes/24 hours; Grade 2 = Some interference with activity or > 2 episodes/24 hours; Grade 3 = Prevents daily activity, requires outpatient IV hydration; Grade 4 = ER visit or hospitalization for hypotensive shock.
l Any Grade = any event that is ≥ Grade 1, where Grade 1 = 38.0 – 38.4°C (100.4 – 101.1°F); Grade 2 = 38.5 – 38.9°C (101.2 – 102.0°F); Grade 3 = 39.0 – 40°C (102.1 – 104°F); Grade 4 = > 40°C (> 104°F).

Unsolicited Adverse Events

In Study 1, participants were monitored for unsolicited adverse events from the booster dose through 28 days after the booster dose and for serious adverse events, adverse events of special interest and vaccine-related medically attended events for the duration of study participation. In the booster dose period, 13,353 participants received Novavax COVID-19 Vaccine, Adjuvanted (Original monovalent). Of the participants who received the booster dose, 96% had a follow-up duration of at least 2 months (median 6.7 months) after the booster dose.

From the booster dose through 28 days after the booster dose, the overall frequency of unsolicited adverse events, excluding events collected through a COVID-19 surveillance diary, was 4.7%. From the booster dose through the duration of follow up (median 6.7 months), serious adverse events were reported by 227 (1.7%) participants who received a booster dose of Novavax COVID-19 Vaccine, Adjuvanted (Original monovalent).

One serious event of non-ST elevation myocardial infarction was reported in a 28-year-old male participant 3 days after a booster dose of Novavax COVID-19 Vaccine, Adjuvanted; however, clinical features were also consistent with myocarditis (chest pain and elevated troponin), and no cardiac catheterization or cardiac MRI was performed during the acute presentation.

A serious adverse event of autoimmune hepatitis was reported in a 57-year-old male participant approximately 12 days after a booster dose of Novavax COVID-19 Vaccine, Adjuvanted (Original monovalent). A year prior to vaccination, the participant had transient increases in alanine transferase (ALT), up to 3 times the upper limit of normal (ULN). From a normal baseline ALT prior to receipt of the first dose of Novavax COVID-19 Vaccine, Adjuvanted (Original monovalent), ALT increased to 4 times ULN following the second dose of the primary series. After the booster dose, a recurrent and higher ALT increase was observed (7 times ULN). Viral hepatitis tests were negative, and no alternative etiologies have been identified. The event was ongoing for 8 months and was not resolved with azathioprine treatment. Currently available information for this event is insufficient to determine a causal relationship with the vaccine.

Two serious adverse events in the injected arm were reported, including muscle edema in a 51-year-old female with onset 7 days after booster vaccination and cellulitis of the injection site in a 58-year-old male with onset 3 days after booster vaccination. The cellulitis resolved following antibiotic and steroid treatment. The muscle edema was not responsive to non-steroidal anti-inflammatory agents. The event was reported as not resolved. Available information for these events is insufficient to determine a causal relationship with the vaccine.

A serious adverse event of extensive left leg and pelvic deep vein thrombosis and pulmonary embolism was reported 7 and 10 days, respectively, after booster in a 35-year-old female participant receiving oral contraceptive therapy. She required surgical intervention, thrombolytic therapy and prolonged anti-coagulation. Available information for this event is insufficient to determine a causal relationship with the vaccine.

2-Dose Series (Vaccine with a Different Manufacturing Process) in Vaccine-Naïve Adults

Study 2 was a randomized (1:1), placebo-controlled study that included a crossover design, with 10,795 participants who received at least one dose of a COVID-19 vaccine containing SARS-CoV-2 recombinant spike protein and Matrix-M adjuvant, manufactured by a different process than Novavax COVID-19 Vaccine, Adjuvanted (Original monovalent) evaluated in Study 1, and 10,864 participants who received at least one dose of placebo.

A serious event of Guillain Barré syndrome was reported 9 days following administration of Dose 1 of the vaccine. No events of Guillain Barré syndrome were reported following administration of placebo.

In Studies 3 and 4, approximately 5,500 participants received at least one dose of a COVID-19 vaccine containing SARS-CoV-2 recombinant spike protein and Matrix-M adjuvant, manufactured by a different process than Novavax COVID-19 Vaccine, Adjuvanted (Original monovalent) evaluated in Study 1. No serious adverse events considered related to vaccination were reported in these studies.

Myocarditis and/or pericarditis were reported in Study 2 and were not reported in Studies 3 and 4. In Study 2, serious events of myocarditis in a 19-year-old male and pericarditis in a 60-year-old female were reported 3 days following administration of Dose 2 and 11 days following Dose 1, respectively, of Novavax COVID-19 Vaccine, Adjuvanted (Original monovalent). No events of myocarditis or pericarditis were reported following administration of placebo.

Single Dose (Original Monovalent, Monovalent Omicron BA.1, or Bivalent Original and Omicron BA.1) in Vaccine-Experienced Adults

The safety of a Novavax COVID-19 Vaccine, Adjuvanted (Original monovalent) booster dose in individuals who completed a primary vaccination with another authorized or approved COVID-19 vaccine (heterologous booster dose) is inferred from the safety of a Novavax COVID-19 Vaccine, Adjuvanted (Original monovalent) booster dose administered following completion of a Novavax COVID-19 Vaccine, Adjuvanted (Original monovalent) primary series (homologous booster dose) and from a clinical study conducted in the US (NCT05463068; Study 5). This was a Phase 3, randomized study comparing 3 different lots of Novavax COVID-19 Vaccine, Adjuvanted (Original monovalent) in 905 adults 18 through 49 years of age who had been previously vaccinated with a primary series of an authorized/approved COVID-19 vaccine with or without a booster, at least 6 months before receiving Novavax COVID-19 Vaccine, Adjuvanted (Original monovalent). Most participants were previously vaccinated with Pfizer-BioNTech (57%) or Moderna (34%) COVID-19 Vaccines.

The safety of Novavax COVID-19 Vaccine, Adjuvanted (Original monovalent), Monovalent Vaccine (Omicron BA.1) and Bivalent Vaccine (Original monovalent and Omicron BA.1) administered as a booster dose to individuals 18 through 64 years of age, previously vaccinated with three doses of an authorized or approved mRNA COVID-19 vaccine was assessed in a randomized, observer blind study (NCT05372588, Part 1 in Australia; Study 6).

The safety analysis set included 274 participants in the Novavax COVID-19 Vaccine, Adjuvanted (Original monovalent) group, 286 participants in the Monovalent Vaccine (Omicron BA.1) group, and 269 participants in the Bivalent Vaccine (Original monovalent and Omicron BA.1) group. The median time since the last COVID-19 vaccination was 180.0 days. The median age of the population was 41 years (range 18 – 64); 727 (87.7%) participants were 18 through 54 years of age and 102 (12.3%) were 55 years and older. Overall, 46.1% were male, 53.9% were female; 2.4% were Hispanic or Latino; 80.6% were White, 0.2% were African American, 0.6% were Aboriginal Australian, 14.6% were Asian, 0.2% were Native Hawaiian or Pacific Islander, 2.7% were other races, and 1.1% were Multiracial. Demographic characteristics were similar across the three groups.

In Study 5, participants were monitored for medically attended unsolicited adverse events through 28 days after the booster dose. The overall frequency of these events was 4.3% and was similar for those previously vaccinated with either Pfizer-BioNTech or Moderna COVID-19 Vaccines. Serious adverse events were reported by 2 (0.2%) participants, with no events of myocarditis and/or pericarditis.

In Study 6, Part 1, participants were monitored through 28 days after the booster dose for unsolicited adverse events and through end of study (median duration of follow-up was 244 days) for serious adverse events. In the 28 days after vaccination, unsolicited adverse events were reported by 32.2%, 38.3% and 33.5% of participants who received the Monovalent Vaccine (Omicron BA.1), Novavax COVID-19 Vaccine, Adjuvanted (Original monovalent), and Bivalent Vaccine (Original monovalent and Omicron BA.1), respectively. No unsolicited adverse events were severe and considered related to vaccine.

Serious adverse events were reported by 8 participants (8/286, 2.8%) in the Monovalent Vaccine (Omicron BA.1) group, 4 participants (4/274, 1.5%) in the Novavax COVID-19 Vaccine, Adjuvanted (Original monovalent) group, and 4 participants (4/269, 1.5%) in the Bivalent Vaccine (Original monovalent and Omicron BA.1) group. None of these serious adverse events were considered related to vaccination.

Single Dose (Original Monovalent, Monovalent Omicron BA.5, or Bivalent Original and Omicron BA.5) in Vaccine-Experienced Adults

The safety of Novavax COVID-19 Vaccine, Adjuvanted (Original monovalent), the Monovalent Vaccine (Omicron BA.5), and the Bivalent Vaccine (Original monovalent and Omicron BA.5) administered as a booster dose to individuals 18 years of age and older previously vaccinated with three or more doses of an authorized or approved mRNA COVID-19 vaccine was assessed in a randomized, observer blind study (NCT05372588, Part 2 in Australia; Study 6).

The safety analysis set included 251 participants in the Novavax COVID-19 Vaccine, Adjuvanted (Original monovalent) group, 254 participants in the Monovalent Vaccine (Omicron BA.5) group and 259 participants in the Bivalent Vaccine (Original monovalent and Omicron BA.5) group. The median time since the last COVID-19 vaccination was 352.5 days. The median age of the population was 43 years (range 18 – 83); 632 (82.7%) participants were 18 through 54 years of age and 132 (17.3%) were 55 years and older. Overall, 45.0% were male, 55.0% were female; 2.1% were Hispanic or Latino; 80.5% were White, 0.3% were African American, 2.0% were Aboriginal Australian, 12.3% were Asian, 0.7% were Native Hawaiian or Pacific Islander, 3.1% were other races, and 0.9% were Multiracial. Demographic characteristics were similar across the three groups. Safety analysis included a median follow-up of 220 days post booster dose through data extraction of 07 February 2024. The safety follow-up is ongoing.

Solicited Adverse Reactions

Local and systemic adverse reactions were solicited within 7 days following vaccination with Novavax COVID-19 Vaccine, Adjuvanted (Original monovalent), the Monovalent Vaccine (Omicron BA.5), or the Bivalent Vaccine (Original monovalent and Omicron BA.5) using an electronic diary. In Study 6, in participants who had previously received authorized or approved mRNA Covid-19 vaccines, the percentages and types of reported solicited local and systemic adverse reactions were consistent with those reported by participants following administration of the Original Monovalent vaccine as presented in Table 4.

Unsolicited Adverse Events

Participants were monitored through 28 days after the booster dose for unsolicited adverse events and through end of study (median duration of follow-up was 220 days) for AESIs, serious adverse events, and treatment related medically attended adverse events. In the 28 days after 1 dose of study vaccine, unsolicited adverse events were reported by 19.7%, 25.9%, and 20.8% of participants who received the Monovalent Vaccine (Omicron BA.5), Novavax COVID-19 Vaccine (Original monovalent), and the Bivalent Vaccine (Original monovalent and Omicron BA.5), respectively. One unsolicited severe, related nonserious adverse event of diarrhea was reported.

Serious adverse events were reported by 7 participants (7/254, 2.8%) in the Monovalent Vaccine (Omicron BA.5) group, 10 participants (10/251, 4.0%) in the Novavax COVID-19 Vaccine, Adjuvanted (Original monovalent) group, and 3 participants (3/259, 1.2%) in the Bivalent Vaccine (Original monovalent and Omicron BA.5) group.

Two participants reported serious adverse events of cranial nerve palsy, including a serious adverse event of fourth cranial nerve palsy with onset of symptoms 7 days post vaccination and a serious adverse event of sixth cranial nerve palsy with onset of symptoms 14 days post vaccination. Both participants had predisposing risk factors, including diabetes, hypertension, and hypercholesterolemia. Currently available information on oculomotor cranial palsies is insufficient to determine a causal relationship with the vaccine.

One participant reported a serious adverse event of vestibular neuronitis (eighth cranial nerve), which occurred twice (11 days after dose one and 16 days after dose two of study vaccine), and was assessed as related to the vaccine.

Single Dose (Monovalent Omicron XBB.1.5) in Vaccine-Naïve Adults with Evidence of Prior SARS-CoV-2 Infection and in Vaccine-Experienced Adults

The safety of Novavax COVID-19 Vaccine, Adjuvanted (2023-2024 Formula) administered as a single dose in baseline SARS-CoV-2 seropositive and COVID-19 vaccine-naïve individuals 18 years of age and older was assessed in an open-label study in the US and US territories (NCT05975060, Part 2; Study 7).

The safety analysis set included 338 participants. The median age of the population was 38 years (range 18 to 75 years); 284 (84.0%) participants were 18 through 54 years of age, and 54 (16.0%) were 55 years and older. Overall, 56.2% were female, 43.8% were male; 49.4% were White, 43.5% were Black or African American, 1.8% were American Indian or Alaskan Native, 0.3% were Native Hawaiian or Other Pacific Islander, 0.6% were Asian, 0.9% were other races, and 1.5% were Multiracial; 25.7% were Hispanic or Latino. Safety analysis included a median follow-up of 171 days post single-dose vaccination through end of study.

Solicited Adverse Reactions

Local and systemic adverse reactions were solicited within 7 days following single-dose vaccination with Novavax COVID-19 Vaccine, Adjuvanted (2023-2024 Formula) in COVID-19 vaccine-naïve adult participants. The reported frequency and severity of solicited local and systemic adverse reactions in participants 18 years of age and older are presented in Table 5.

Table 5: Number and Percentage of Participants with Soliciteda Local and Systemic Adverse Reactions Starting within 7b Days After a Single Dose in Participants 18 Years of Age and Older in COVID-19 Vaccine-naïve Adult Participants, Study 7 (Safety Analysis Set)c
Event | Novavax COVID-19 Vaccine, Adjuvanted (2023-2024 Formula) Single Dose
 | N=338 n (%)
Local Adverse Reactionsd
Tendernesse
Any Grade | 129 (38.2)
Grade 3 | 3 (0.9)
Painf
Any Grade | 85 (25.1)
Grade 3 | 2 (0.6)
Redness (erythema)g
Any Grade | 4 (1.2)
Swellingh
Any Grade | 1 (0.3)
Systemic Adverse Reactionsd
Muscle paini
Any Grade | 106 (31.4)
Grade 3 | 4 (1.2)
Headachej
Any Grade | 92 (27.2)
Grade 3 | 3 (0.9)
Fatiguei
Any Grade | 80 (23.7)
Grade 3 | 3 (0.9)
Malaisei
Any Grade | 48 (14.2)
Grade 3 | 3 (0.9)
Joint paini
Any Grade | 44 (13.0)
Grade 3 | 2 (0.6)
Nausea/vomitingk
Any Grade | 42 (12.4)
Grade 3 | 2 (0.6)
Feverl
Any Grade | 3 (0.9)
a Solicited reactogenicity events and use of antipyretic or pain medication were collected by the participant in the electronic diary (eDiary).
b 7 days included day of vaccination and the subsequent 6 days.
c The analysis included a total of 338 participants who received a single dose and completed at least one day of the vaccination reactogenicity diary, reported an unsolicited adverse event that was mapped to a reactogenicity term within 7 days of the dose, reported a symptom in the Daily Illness Symptoms Diary that was mapped to a reactogenicity term within 7 days of the dose, or reported a temperature in the Daily Illness Symptoms Diary within 7 days of the dose.
d Absence of rows for Grade 3 or Grade 4 adverse reactions indicates no events were reported.
e Any Grade = any event that is ≥ Grade 1, where Grade 1 = Mild discomfort to touch; Grade 2 = Discomfort with movement; Grade 3 = Significant discomfort at rest; Grade 4 = Emergency room (ER) visit or hospitalization.
f Any Grade = any event that is ≥ Grade 1, where Grade 1 = Does not interfere with activity; Grade 2 = Repeated use of non-narcotic pain reliever > 24 hours or interferes with activity; Grade 3 = Any use of narcotic pain reliever or prevents daily activity; Grade 4 = ER visit or hospitalization.
g Any Grade = any event that is ≥ Grade 1, where Grade 1 = 2.5 – 5 cm; Grade 2 = 5.1 – 10 cm; Grade 3 = > 10 cm; Grade 4 = Necrosis or exfoliative dermatitis.
h Any Grade = any event that is ≥ Grade 1, where Grade 1 = 2.5 – 5 cm and does not interfere with activity; Grade 2 = 5.1 – 10 cm or interferes with activity; Grade 3 = > 10 cm or prevents daily activity; Grade 4 = Necrosis.
i Any Grade = any event that is ≥ Grade 1, where Grade 1 = No interference with activity; Grade 2 = Some interference with activity; Grade 3 = Significant; prevents daily activity; Grade 4 = ER visit or hospitalization.
j Any Grade = any event that is ≥ Grade 1, where Grade 1 = No interference with activity; Grade 2 = Repeated use of non-narcotic pain reliever > 24 hours or some interference with activity; Grade 3 = Significant; any use of narcotic pain reliever or prevents daily activity; Grade 4 = ER visit or hospitalization.
k Any Grade = any event that is ≥ Grade 1, where Grade 1 = No interference with activity or 1 – 2 episodes/24 hours; Grade 2 = Some interference with activity or > 2 episodes/24 hours; Grade 3 = Prevents daily activity, requires outpatient IV hydration; Grade 4 = ER visit or hospitalization for hypotensive shock.
l Any Grade = any event that is ≥ Grade 1, where Grade 1 = 38.0 – 38.4°C (100.4 – 101.1°F); Grade 2 = 38.5 – 38.9°C (101.2 – 102.0°F); Grade 3 = 39.0 – 40°C (102.1 – 104°F); Grade 4 = > 40°C (> 104°F).

Unsolicited Adverse Events (non-serious and serious)

Participants were monitored through 28 days after single-dose vaccination for unsolicited adverse events. Of the 338 participants who received a dose of study vaccine, unsolicited adverse events were reported by 5.3% of participants. Of these, 1 participant reported a non-serious unsolicited adverse event considered related to the study vaccine (heavy menstrual bleeding), and 1 participant reported a serious adverse event (obstructive pancreatitis) assessed as severe in intensity and not related to vaccination.

Serious adverse events were reported by 5 (1.5%) participants after single-dose vaccination with Novavax COVID-19 Vaccine, Adjuvanted (2023-2024 Formula) through end of study (median duration of follow-up was 171 days), and none were assessed as related to study vaccine.

CLINICAL TRIALS EXPERIENCE

Adolescents 12 Years Through 17 Years of Age

Safety of Novavax COVID-19 Vaccine, Adjuvanted (Original monovalent) in adolescents was assessed in the adolescent part of Study 1 conducted in the US. In this study, 2,153 participants 12 through 17 years of age received at least one primary series dose of Novavax COVID-19 Vaccine, Adjuvanted (Original monovalent).

2-Dose Series (Original Monovalent) in Vaccine-Naïve Adolescents

Study 1 was a Phase 3, multicenter, randomized (2:1), observer-blinded, placebo-controlled, crossover study adolescent participants 12 through 17 years of age in the US. Participants were randomized (2:1) to receive 2 doses of the vaccine or placebo administered 21 days apart.

In the adolescent part of Study 1, participants 12 through 17 years of age received at least one dose of vaccine (n=1,487) or placebo (n=745) in the pre-crossover period; 50.8% were male, 49.2% were female; 75.0% were White, 13.6% were Black or African American, 2.9% were Asian, 2.2% were American Indian (including Native Americans) or Alaskan Native, and 5.5% were multiple races; 18.4% were Hispanic/Latino. Demographic characteristics were similar between the Novavax COVID-19 Vaccine, Adjuvanted (Original monovalent) and placebo groups. During the study, COVID-19 vaccines authorized for emergency use became available, and participants, when eligible for vaccination, were offered the opportunity to cross over from the originally assigned study treatment to the other study treatment (vaccine or placebo) in a blinded fashion (“blinded crossover”). In the post-crossover period, 666 participants received Novavax COVID-19 Vaccine, Adjuvanted (Original monovalent), and 1,354 participants received placebo. The demographic characteristics were similar between participants in the pre-crossover and post-crossover groups.

Solicited Adverse Reactions

During the pre-crossover period, local and systemic adverse reactions were solicited within 7 days following each dose of Novavax COVID-19 Vaccine, Adjuvanted (Original monovalent) or placebo in participants using an electronic diary.

The reported frequency and severity of solicited local and systemic adverse reactions in participants 12 through 17 years of age are presented in Table 6.

Table 6: Number and Percentage of Participants with Soliciteda Local and Systemic Adverse Reactions Starting Within 7 Daysb After Each Dose in Participants 12 through 17 Years of Age, Study 1 (Solicited Safety Set, Dose 1 and Dose 2)c
Event | Novavax COVID-19 Vaccine, Adjuvanted (Original Monovalent) |  | Placebod
Event | Dose 1 N=1,448 n (%) | Dose 2 N=1,394 n (%) | Dose 1 N=726 n (%) | Dose 2 N=686 n (%)
Local Adverse Reactionse
Tendernessf
Any Grade | 819 (56.6) | 909 (65.2) | 153 (21.1) | 97 (14.1)
Grade 3 | 16 (1.1) | 93 (6.7) | 2 (0.3) | 1 (0.1)
Paing
Any Grade | 647 (44.7) | 850 (61.0) | 126 (17.4) | 102 (14.9)
Grade 3 | 10 (0.7) | 38 (2.7) | 2 (0.3) | 3 (0.4)
Swellingh
Any Grade | 20 (1.4) | 111 (8.0) | 3 (0.4) | 1 (0.1)
Grade 3 | 0 | 8 (0.6) | 0 | 0
Redness (erythema)i
Any Grade | 15 (1.0) | 104 (7.5) | 5 (0.7) | 0
Grade 3 | 0 | 10 (0.7) | 0 | 0
Systemic Adverse Reactionse
Muscle pain (myalgia)j
Any Grade | 492 (34.0) | 684 (49.1) | 114 (15.7) | 82 (12.0)
Grade 3 | 17 (1.2) | 104 (7.5) | 4 (0.6) | 6 (0.9)
Headachek
Any Grade | 440 (30.4) | 793 (56.9) | 181 (24.9) | 119 (17.3)
Grade 3 | 13 (0.9) | 87 (6.2) | 12 (1.7) | 14 (2.0)
Grade 4 | 0 | 1 (< 0.1) | 0 | 0
Fatiguej
Any Grade | 350 (24.2) | 696 (49.9) | 112 (15.4) | 100 (14.6)
Grade 3 | 23 (1.6) | 189 (13.6) | 9 (1.2) | 11 (1.6)
Malaisej
Any Grade | 215 (14.8) | 560 (40.2) | 67 (9.2) | 51 (7.4)
Grade 3 | 16 (1.1) | 126 (9.0) | 7 (1.0) | 4 (0.6)
Nausea or vomitingl
Any Grade | 113 (7.8) | 277 (19.9) | 56 (7.7) | 33 (4.8)
Grade 3 | 2 (0.1) | 14 (1.0) | 3 (0.4) | 3 (0.4)
Grade 4 | 0 | 1 (< 0.1) | 0 | 0
Joint pain (arthralgia)j
Any Grade | 102 (7.0) | 225 (16.1) | 35 (4.8) | 21 (3.1)
Grade 3 | 6 (0.4) | 40 (2.9) | 1 (0.1) | 2 (0.3)
Feverm
Any Grade | 9 (0.6) | 235 (16.9) | 4 (0.6) | 1 (0.1)
Grade 3 | 1 (< 0.1) | 31 (2.2) | 0 | 0
a Solicited reactogenicity events and use of antipyretic or pain medication were recorded by participants’ parent(s)/caregiver(s) and collected in the electronic diary (eDiary).
b 7 days included day of vaccination and the subsequent 6 days.
c The analysis included 1,448 (Dose 1) and 1,394 (Dose 2) participants in the Novavax COVID-19 Vaccine, Adjuvanted (Original monovalent) group and 726 (Dose 1) and 686 (Dose 2) participants in the placebo group who received at least one dose and completed at least one day of the vaccination reactogenicity diary, reported an unsolicited adverse event that was mapped to a reactogenicity term within 7 days of the dose, reported a symptom in the paper memory aid of COVID symptoms that was mapped to a reactogenicity term within 7 days of the dose, or reported a temperature in the paper memory aid of COVID symptoms within 7 days of the dose.
d Placebo was a saline solution.
e Absence of rows for Grade 4 adverse reactions indicates no events were reported.
f Any Grade = any event that is ≥ Grade 1, where Grade 1 = Mild discomfort to touch; Grade 2 = Discomfort with movement; Grade 3 = Significant discomfort at rest; Grade 4 = Emergency room (ER) visit or hospitalization.
g Any Grade = any event that is ≥ Grade 1, where Grade 1 = Does not interfere with activity; Grade 2 = Repeated use of non-narcotic pain reliever > 24 hours or interferes with activity; Grade 3 = Any use of narcotic pain reliever or prevents daily activity; Grade 4 = ER visit or hospitalization.
h Any Grade = any event that is ≥ Grade 1, where Grade 1 = 2.5 – 5 cm and does not interfere with activity; Grade 2 = 5.1 – 10 cm or interferes with activity; Grade 3 = > 10 cm or prevents daily activity; Grade 4 = Necrosis.
i Any Grade = any event that is ≥ Grade 1, where Grade 1 = 2.5 – 5 cm; Grade 2 = 5.1 – 10 cm; Grade 3 = > 10 cm; Grade 4 = Necrosis or exfoliative dermatitis.
j Any Grade = any event that is ≥ Grade 1, where Grade 1 = No interference with activity; Grade 2 = Some interference with activity; Grade 3 = Significant; prevents daily activity; Grade 4 = ER visit or hospitalization.
k Any Grade = any event that is ≥ Grade 1, where Grade 1 = No interference with activity; Grade 2 = Repeated use of non-narcotic pain reliever > 24 hours or some interference with activity; Grade 3 = Significant; any use of narcotic pain reliever or prevents daily activity; Grade 4 = ER visit or hospitalization.
l Any Grade = any event that is ≥ Grade 1, where Grade 1 = No interference with activity or 1 – 2 episodes/24 hours; Grade 2 = Some interference with activity or > 2 episodes/24 hours; Grade 3 = Prevents daily activity, requires outpatient IV hydration; Grade 4 = ER visit or hospitalization for hypotensive shock.
m Any Grade = any event that is ≥ Grade 1, where Grade 1 = 38.0 – 38.4°C (100.4 – 101.1°F); Grade 2 = 38.5 – 38.9°C (101.2 – 102.0°F); Grade 3 = 39.0 – 40°C (102.1 – 104°F); Grade 4 = > 40°C (> 104°F).

CLINICAL TRIALS EXPERIENCE

Unsolicited Adverse Events

In Study 1, participants were monitored for unsolicited adverse events from the first dose through 28 days after the second dose in both the pre- and post-crossover periods and for serious adverse events, AESIs and vaccine-related medically attended adverse events for the duration of study participation. Participants who received at least one dose in the pre- or post-crossover periods were included in the safety analysis. In the pre-crossover period 1,487 participants received Novavax COVID-19 Vaccine, Adjuvanted (Original monovalent) and 745 participants received placebo. In the post-crossover period, 666 participants received Novavax COVID-19 Vaccine, Adjuvanted (Original monovalent) and 1,354 received placebo. Of participants who received two doses of Novavax COVID-19 Vaccine, Adjuvanted (Original monovalent) in the pre-crossover period (n=1,468), 86% had a follow-up duration of at least 2 months (median = 71 days) after Dose 2. Of participants who received two doses of Novavax COVID-19 Vaccine, Adjuvanted (Original monovalent) in the post-crossover period (n=658), 99.7% had a follow-up duration of at least 2 months (median = 234 days) after the last dose.

From Dose 1 through 28 days following Dose 2 in the pre-crossover period, the overall frequency of unsolicited adverse events was 15.8% in the Novavax COVID-19 Vaccine, Adjuvanted (Original monovalent) group vs 16.0% in the placebo group. From Dose 1 through 28 days following Dose 2 in the post-crossover period, the overall frequency of unsolicited adverse events was 17.1% in the Placebo/Novavax COVID-19 Vaccine, Adjuvanted (Original monovalent) group vs 14.6% in the Novavax COVID-19 Vaccine, Adjuvanted (Original monovalent)/Placebo group. In an analysis of all unsolicited adverse events reported following any dose, through 28 days following Dose 2, those assessed as adverse reactions not already captured by solicited local and systemic reactions in the Novavax COVID-19 Vaccine, Adjuvanted (Original monovalent) group and placebo group were lymphadenopathy (0.7% vs 0 pre-crossover and 0.2% vs 0.2% post-crossover) and chills (0.3% vs 0.3% pre-crossover and 0.6% vs 0.1% post-crossover), respectively.

In the pre-crossover period, serious adverse events were reported by 7 (0.5%) participants in the Novavax COVID-19 Vaccine, Adjuvanted (Original monovalent) group and by 2 (0.3%) participants in the placebo group. In the post-crossover period, serious adverse events were reported by 8 (1.2%) participants who received Placebo/Novavax COVID-19 Vaccine, Adjuvanted (Original monovalent) and by 11 (0.8%) participants who received Novavax COVID-19 Vaccine, Adjuvanted (Original monovalent)/Placebo.

A total of one event of myocarditis was reported by one (0.05%) participant after Novavax COVID-19 Vaccine, Adjuvanted (Original monovalent) and no events were reported by participants after placebo. One serious adverse event of myocarditis was reported by a 16-year-old male 2 days after Dose 2.

Single Dose (Original Monovalent) in Vaccine-Experienced Adolescents

In an open-label portion of Study 1, 1,495 participants 12 through 17 years of age received a single booster dose of Novavax COVID-19 Vaccine, Adjuvanted (Original monovalent) (0.5 mL) at least 5 months after the two-dose primary series (median of 10.3 months between completion of primary series and booster dose); an additional 4 participants received the dose without having completed the two-dose primary series. Safety analyses included evaluation of solicited local and systemic adverse reactions within 7 days after a booster dose for participants who completed the electronic diary (n=1,256) and unsolicited adverse events within 28 days after a booster dose (n=1,499). Safety analysis also included evaluation of serious adverse events, adverse events of special interest and vaccine-related medically attended events after a booster dose (n=1,499) with a median follow-up of 3.4 months post booster dose. The safety follow-up is ongoing.

Among the 1,499 adolescent participants, 53.8% were male, 46.2% were female; 73.1% were White, 14.6% were Black or African American, 3.5% were Asian, 2.7% were American Indian (including Native Americans) or Alaskan Native, 0.3% were Native Hawaiian or Other Pacific Islander, and 5.1% were multiple races; 18.4% were Hispanic or Latino.

Solicited Adverse Reactions

Local and systemic adverse reactions were solicited within 7 days following the booster dose of Novavax COVID-19 Vaccine, Adjuvanted (Original monovalent) using an electronic diary.

The reported frequency and severity of solicited local and systemic adverse reactions in a subset of participants 12 years through 17 years of age are presented in Table 7.

Table 7: Number and Percentage of Participants with Soliciteda Local and Systemic Adverse Reactions Starting Within 7 Daysb After Booster Dose in Participants 12 Years Through 17 Years of Age, Study 1 (Booster Safety Analysis Set)c
Event | Novavax COVID-19 Vaccine, Adjuvanted (Original Monovalent) Booster N=1,256 n (%)
Local Adverse Reactionsd
Tendernesse
Any Grade | 828 (65.9)
Grade 3 | 116 (9.2)
Grade 4 | 1 (< 0.1)
Painf
Any Grade | 812 (64.6)
Grade 3 | 61 (4.9)
Redness (erythema)g
Any Grade | 129 (10.3)
Grade 3 | 29 (2.3)
Swellingh
Any Grade | 119 (9.5)
Grade 3 | 18 (1.4)
Systemic Adverse Reactionsd
Headachei
Any Grade | 790 (62.9)
Grade 3 | 154 (12.3)
Grade 4 | 2 (0.2)
Muscle pain (myalgia)j
Any Grade | 758 (60.4)
Grade 3 | 143 (11.4)
Grade 4 | 1 (< 0.1)
Fatiguej
Any Grade | 717 (57.1)
Grade 3 | 216 (17.2)
Grade 4 | 1 (< 0.1)
Malaisej
Any Grade | 566 (45.1)
Grade 3 | 170 (13.5)
Grade 4 | 1 (< 0.1)
Nausea or vomitingk
Any Grade | 296 (23.6)
Grade 3 | 20 (1.6)
Joint pain (arthralgia)j
Any Grade | 275 (21.9)
Grade 3 | 50 (4.0)
Grade 4 | 1 (< 0.1)
Feverl
Any Grade | 211 (16.8)
Grade 3 | 44 (3.5)
Grade 4 | 3 (0.2)
a Solicited reactogenicity events and use of antipyretic or pain medication were recorded by participants’ parent(s)/caregiver(s) and collected in the electronic diary (eDiary).
b 7 days included day of vaccination and the subsequent 6 days.
c The analysis included a total of 1,256 participants who received the booster dose and completed at least one day of the reactogenicity diary, reported an unsolicited adverse event that was mapped to a reactogenicity term within 7 days of the dose, reported a symptom in the paper memory aid of COVID symptoms that was mapped to a reactogenicity term within 7 days of the dose, or reported a temperature in the paper memory aid of COVID symptoms within 7 days of the dose
d Absence of rows for Grade 4 adverse reactions indicates no events were reported.
e Any Grade = any event that is ≥ Grade 1, where Grade 1 = Mild discomfort to touch; Grade 2 = Discomfort with movement; Grade 3 = Significant discomfort at rest; Grade 4 = Emergency room (ER) visit or hospitalization.
f Any Grade = any event that is ≥ Grade 1, where Grade 1 = Does not interfere with activity; Grade 2 = Repeated use of non-narcotic pain reliever > 24 hours or interferes with activity; Grade 3 = Any use of narcotic pain reliever or prevents daily activity; Grade 4 = ER visit or hospitalization.
g Any Grade = any event that is ≥ Grade 1, where Grade 1 = 2.5 – 5 cm; Grade 2 = 5.1 – 10 cm; Grade 3 = > 10 cm; Grade 4 = Necrosis or exfoliative dermatitis.
h Any Grade = any event that is ≥ Grade 1, where Grade 1 = 2.5 – 5 cm and does not interfere with activity; Grade 2 = 5.1 – 10 cm or interferes with activity; Grade 3 = > 10 cm or prevents daily activity; Grade 4 = Necrosis.
i Any Grade = any event that is ≥ Grade 1, where Grade 1 = No interference with activity; Grade 2 = Repeated use of non-narcotic pain reliever > 24 hours or some interference with activity; Grade 3 = Significant; any use of narcotic pain reliever or prevents daily activity; Grade 4 = ER visit or hospitalization.
j Any Grade = any event that is ≥ Grade 1, where Grade 1 = No interference with activity; Grade 2 = Some interference with activity; Grade 3 = Significant; prevents daily activity; Grade 4 = ER visit or hospitalization.
k Any Grade = any event that is ≥ Grade 1, where Grade 1 = No interference with activity or 1 – 2 episodes/24 hours; Grade 2 = Some interference with activity or > 2 episodes/24 hours; Grade 3 = Prevents daily activity, requires outpatient IV hydration; Grade 4 = ER visit or hospitalization for hypotensive shock.
l Any Grade = any event that is ≥ Grade 1, where Grade 1 = 38.0 – 38.4°C (100.4 – 101.1°F); Grade 2 = 38.5 – 38.9°C (101.2 – 102.0°F); Grade 3 = 39.0 – 40°C (102.1 – 104°F); Grade 4 = > 40°C (> 104°F).

Unsolicited Adverse Events

In Study 1, participants were monitored for unsolicited adverse events from the booster dose through 28 days after the booster dose and for serious adverse events, adverse events of special interest and vaccine-related medically attended events for the duration of study participation. In the booster dose period, 1,499 adolescent participants received Novavax COVID-19 Vaccine, Adjuvanted (Original monovalent). Of the participants who received the booster dose, 98% had a follow-up duration of at least 2 months (median 6.6 months) after the booster dose. From the booster dose through 28 days after the booster dose, the proportion of participants reporting an unsolicited adverse event was 6.4% and the proportion of participants reporting lymphadenopathy was 0.4%.

Serious adverse events in the boosted population of 1,499 participants were reported by 19 (1.3%) participants who received a booster dose of Novavax COVID-19 Vaccine, Adjuvanted (Original monovalent), with no reported events of myocarditis and/or pericarditis.

6.2 Postmarketing Experience

The following adverse reactions have been identified during post-authorization use of Novavax COVID-19 Vaccine, Adjuvanted. Because these reactions are reported voluntarily from a population of uncertain size, it is not always possible to reliably estimate their frequency or establish a causal relationship to vaccine exposure.

Cardiac Disorders: myocarditis, pericarditis

Immune System Disorders: anaphylaxis

Nervous System Disorders: paresthesia, hypoesthesia

8 USE IN SPECIFIC POPULATIONS

8.1 Pregnancy

Pregnancy Exposure Registry

There is a pregnancy exposure registry that monitors pregnancy outcomes in women exposed to NUVAXOVID during pregnancy. Women who are vaccinated with NUVAXOVID during pregnancy are encouraged to enroll in the registry by visiting https://c-viper.pregistry.com/.

Risk Summary

All pregnancies have a risk of birth defect, loss, or other adverse outcomes. In the US general population, the estimated background risk of major birth defects and miscarriage in clinically recognized pregnancies is 2% to 4% and 15% to 20%, respectively. Available data on NUVAXOVID administered to pregnant women are insufficient to inform vaccine-associated risks in pregnancy.

A developmental toxicity study was performed in female rats administered a vaccine formulation containing the same quantity of SARS-CoV-2 recombinant spike protein and one-fifth the quantity of adjuvant and formulation buffer inactive ingredients included in Novavax COVID-19 Vaccine, Adjuvanted (Original monovalent) on four occasions, twice prior to mating and twice during gestation. The study revealed no evidence of harm to the fetus due to the vaccine (see Animal Data).

Clinical Considerations

Disease-Associated Maternal and/or Embryo/Fetal Risk

Pregnant women infected with SARS-CoV-2 are at increased risk of severe COVID-19 compared with non-pregnant individuals.

Data

Animal Data

In a developmental toxicology study, 0.1 mL of a vaccine formulation containing the same quantity of SARS-CoV-2 rS protein (5 mcg), one-fifth the quantity of adjuvant (10 mcg), and inactive ingredients which comprise the formulation buffer [25 mM sodium phosphate, 300 mM sodium chloride, and 0.01% (w/v) polysorbate 80] contained in a single dose of the Novavax COVID-19 Vaccine, Adjuvanted (Original monovalent) was administered to female rats by the intramuscular route on four occasions: 27 and 13 days prior to mating, and on gestational days 7 and 15. No vaccine-related adverse effects on female fertility, fetal development, or postnatal development were reported in this study.

8.2 Lactation

Risk Summary

It is not known whether NUVAXOVID is excreted in human milk. Data are not available to assess the effects of NUVAXOVID on the breastfed infant or on milk production/excretion. The developmental and health benefits of breastfeeding should be considered along with the mother’s clinical need for NUVAXOVID and any potential adverse effects on the breastfed child from NUVAXOVID or from the underlying maternal condition. For preventive vaccines, the underlying maternal condition is susceptibility to disease otherwise prevented by the vaccine.

8.4 Pediatric Use

The safety and effectiveness of NUVAXOVID in adolescents 12 through 17 years of age with at least one underlying condition that puts them at high risk for severe outcomes from COVID-19 is based on safety and effectiveness data in this age group and in adults [see Adverse Reactions (6) and Clinical Studies (14.2)].

The safety and effectiveness of NUVAXOVID in individuals younger than 12 years of age have not been established.

8.5 Geriatric Use

In a clinical study (Study 1), out of 19,735 subjects who received primary vaccination with Novavax COVID-19 Vaccine, Adjuvanted (Original monovalent), 12.6% (n=2,480) were 65 years of age and older and 1.8% (n=361) were 75 years of age and older. Overall, there were no notable differences in the safety profiles observed between participants 65 years of age and older and younger participants [see Adverse Reactions (6)]. Study 1 did not include sufficient numbers of participants aged 65 years and older to determine whether they respond differently from younger participants [see Clinical Studies (14.1)].

In this study, among subjects who received a booster dose of Novavax COVID-19 Vaccine, Adjuvanted (Original monovalent) (n=13,353), 15.5% (n=2,064) of participants were 65 years of age and older and 2.5% (n=334) of participants were 75 years of age and older. Overall, there were no notable differences in the safety profiles observed between participants 65 years of age and older and younger participants [see Adverse Reactions (6)]. The effectiveness of the booster dose in participants aged 65 years and older was consistent with that observed in participants 18 years through 64 years [see Clinical Studies (14.1)].

Studies 6 and 7 did not include sufficient numbers of patients 65 years of age and older to determine whether they respond differently from younger adult patients.

8.6 Immunocompromised Individuals

The Centers for Disease Control and Prevention has published considerations related to COVID-19 vaccination for individuals who are moderately to severely immunocompromised (https://www.cdc.gov/vaccines/covid-19/clinical-considerations/covid-19-vaccines-us.html).

11 DESCRIPTION

NUVAXOVID (COVID-19 Vaccine, Adjuvanted) is a colorless to slightly yellow, clear to mildly opalescent sterile suspension for intramuscular use that is free from visible particles. Each 0.5 mL dose of NUVAXOVID (2025-2026 Formula) contains 5 mcg of recombinant spike (rS) protein of the SARS-CoV-2 Omicron variant lineage JN.1 and 50 mcg Matrix-M adjuvant. The Matrix-M adjuvant is composed of Fraction-A (42.5 mcg) and Fraction-C (7.5 mcg) of saponin extracts from the soapbark tree, Quillaja saponaria Molina. The rS protein is produced by recombinant DNA technology using a baculovirus expression system in the Sf9 insect cell line that is derived from the Spodoptera frugiperda species.

Each 0.5 mL dose of NUVAXOVID also contains the following ingredients: cholesterol (30.5 mcg), phosphatidylcholine (23 mcg), potassium dihydrogen phosphate (3.85 mcg), potassium chloride (2.25 mcg), disodium hydrogen phosphate dihydrate (14.7 mcg), disodium hydrogen phosphate heptahydrate (2.465 mg), sodium dihydrogen phosphate monohydrate (0.445 mg), sodium chloride (8.766 mg), polysorbate 80 (0.050 mg), and Water for Injection. The pH is adjusted with sodium hydroxide or hydrochloric acid.

Each 0.5 mL dose of NUVAXOVID may also contain residual amounts of baculovirus and Sf9 cell proteins (≤ 0.96 mcg), baculovirus and cellular DNA (≤ 0.00016 mcg), lentil lectin (< 0.025 mcg), methyl-α-D-mannopyranoside (2 mcg), simethicone (< 0.92 mcg), pluronic F-68 (< 2.19 mcg), Triton X-100 (< 0.025 mcg), Tergitol (NP9) (< 0.05 mcg), and DL-α-tocopherol (≤ 0.05 mcg).

NUVAXOVID does not contain a preservative.

The syringe tip cap and plunger stopper are not made with natural rubber latex.

12 CLINICAL PHARMACOLOGY

12.1 Mechanism of Action

NUVAXOVID contains purified, full-length recombinant spike protein. The vaccine elicits an immune response to the recombinant spike protein, which protects against COVID-19.

13 NONCLINICAL TOXICOLOGY

13.1 Carcinogenesis, Mutagenesis, Impairment of Fertility

NUVAXOVID has not been evaluated for the potential to cause carcinogenicity, genotoxicity, or impairment of male fertility.

14 CLINICAL STUDIES

14.1 Adults 18 Years of Age and Older

Efficacy of 2-Dose Series (Original Monovalent) in Vaccine-Naïve Adults

Study 1 adult main study was a Phase 3, multicenter, randomized, observer-blinded, placebo-controlled, crossover study in participants 18 years of age and older in the US and Mexico who were considered to be at higher risk of exposure to and infection with SARS-CoV-2. Eligible participants were medically stable and had no history of previous laboratory-confirmed (by PCR or serology to SARS-CoV-2) diagnosis of SARS-CoV-2 infection or COVID-19 prior to randomization. SARS-CoV-2 PCR samples were tested by a central laboratory. The study excluded individuals who were significantly immunocompromised due to immunodeficiency disease; had received chronic immunosuppressive therapy or had received immunoglobulin or blood-derived products within 90 days; or had a history of laboratory-confirmed diagnosed COVID-19. Individuals with clinically stable underlying comorbidities were included, as were individuals with well-controlled human immunodeficiency virus (HIV) infection. Participants were stratified by age into two strata (18 to < 65 years and ≥ 65 years) and randomized to Novavax COVID-19 Vaccine, Adjuvanted (Original monovalent) or placebo (normal saline) in a 2:1 ratio. A total of 29,943 participants were randomized in a 2:1 ratio to receive two doses of Novavax COVID-19 Vaccine, Adjuvanted (Original monovalent) or placebo 21 days apart. Assessments of safety and efficacy against COVID-19 were conducted for up to 24 months after the second dose.

The primary efficacy analysis population (Per-Protocol Efficacy [PP-EFF] Analysis Set) included 25,510 participants who received a 2-dose series (dose 1 on day 0 and dose 2 on day 21) of either Novavax COVID-19 Vaccine, Adjuvanted (Original monovalent) (n=17,184) or placebo (n=8,326), did not experience an exclusionary protocol deviation, and did not have evidence of SARS-CoV-2 infection at baseline or through 6 days after the second dose.

In the PP-EFF Analysis Set, 48.4% were female; 21.4% were Hispanic or Latino; 75.9% were White, 11.1% were Black or African American, 6.1% were American Indian or Alaska Native, 4.4% were Asian, and 1.7% were Multiracial. 94.2% participants were enrolled at sites in the US and 5.8% participants were enrolled at sites in Mexico. The median age of participants was 47 years (range 18 – 95 years) and 11.7% were 65 years of age and older. Of the study participants in the PP-EFF Analysis Set, 95.2% were at high risk for COVID-19 due to living or working conditions involving known frequent exposure to SARS-CoV-2, comorbidities (chronic lung disease, cardiovascular disease, chronic liver disease, severe obesity, and diabetes), or age ≥ 65 years. Between participants who received Novavax COVID-19 Vaccine, Adjuvanted (Original monovalent) and those who received placebo, there were no notable differences in demographics or pre-existing medical conditions. Participants in the PP-EFF Analysis Set were included in the primary efficacy analysis up until the earliest of the time that they received their crossover vaccination, they received a booster dose (if they did not receive a crossover vaccine) or were censored.

The primary efficacy endpoint was defined as the first PCR-positive symptomatic mild, moderate, or severe COVID-19 illness diagnosed 7 or more days after completion of the second dose of the primary series during the pre-crossover period. Mild COVID-19 was defined as at least one of the following: fever (defined by subjective or objective measure, regardless of use of anti-pyretic medications), new onset of cough, or two or more COVID-19 symptoms (new onset or worsening of shortness of breath or difficulty breathing compared to baseline; new onset fatigue; new onset generalized muscle or body aches; new onset headache; new loss of taste or smell; acute onset of sore throat, congestion or runny nose; new onset nausea, vomiting or diarrhea). Moderate COVID-19 was defined as at least one of the following: high fever (≥ 38.4 °C for ≥ 3 days [regardless of use of anti-pyretic medications, need not be contiguous days]), or any evidence of lower respiratory tract infection (shortness of breath [or breathlessness or difficulty breathing] with or without exertion [greater than baseline]; tachypnea 24 to 29 breaths per minute at rest; SpO2: 94% to 95% on room air; abnormal chest X-ray or chest computerized tomography consistent with pneumonia or lower respiratory tract infection; or adventitious sounds on lung auscultation [i.e., crackles/rales, wheeze, rhonchi, pleural rub, stridor]). Severe COVID-19 was defined as at least one of the following: tachypnea ≥ 30 breaths per minute at rest; resting heart rate ≥ 125 beats per minute; SpO2 ≤ 93% on room air; PaO2/FiO2 < 300 mmHg; high flow oxygen therapy or NIV/NIPPV; mechanical ventilation or extracorporeal membrane oxygenation; evidence of shock (systolic blood pressure < 90 mmHg, diastolic blood pressure < 60 mmHg or requiring vasopressors); significant acute renal, hepatic, cardiac, or neurologic dysfunction or failure; admission to an intensive care unit; or death.

The efficacy of Novavax COVID-19 Vaccine, Adjuvanted (Original monovalent) to prevent PCR-confirmed symptomatic mild, moderate, or severe COVID-19 from 7 days after Dose 2 was 89.6% (95% CI: 82.5%, 93.8%) in participants without evidence of SARS-CoV-2 infection through 6 days after the second dose (see Table 8). The primary efficacy endpoint criterion for success was met as the lower limit of the confidence interval was > 30%. In the PP-EFF Analysis Set, no cases of moderate or severe COVID-19 were reported in participants who had received Novavax COVID-19 Vaccine, Adjuvanted (Original monovalent), compared with eight cases of moderate COVID-19 and four cases of severe COVID-19 that were reported in participants who had received placebo. The PP-EFF Analysis Set had a median follow-up of 2 months post-Dose 2 during the pre-crossover period.

Table 8: Vaccine Efficacy Against PCR-confirmed COVID-19 with Onset from 7 Days After Second Vaccinationa, Study 1 (PP-EFF Analysis Set*)
 | Novavax COVID-19 Vaccine, Adjuvanted (Original Monovalent) |  |  | Placebo |  |  | Vaccine Efficacy (95% CI) (%)
 | Participants N | COVID-19 Cases n (%) | Mean Incidence Rate Per 1,000 Person-Yearsb | Participants N | COVID-19 Cases n (%) | Mean Incidence Rate Per 1,000 Person-Yearsb | Vaccine Efficacy (95% CI) (%)
Primary efficacy endpoint
All participants | 17,184 | 18 (0.1) | 6.0 | 8,326 | 76 (0.9) | 57.2 | 89.6 (82.5, 93.8)c
Mild | – | 18 (0.1) | – | – | 64 (0.8) | – | –
Moderate | – | 0 | – | – | 8 (0.1) | – | –
Severe | – | 0 | – | – | 4 (< 0.1) | – | –
* The PP-EFF Analysis Set had a median follow-up of 2 months post-Dose 2 during the pre-crossover period.
a Vaccine efficacy (VE) evaluated in participants without major protocol deviations who are seronegative (for SARS-CoV-2) at baseline and do not have a laboratory confirmed current SARS-CoV-2 infection with symptom onset through 6 days after the second dose, and who have received two doses of vaccine or placebo as randomized.
b Mean incidence rate per 1,000 person-years was estimated with weighting for age strata reflective of the distribution seen in the study population.
c Based on log-linear model of PCR-confirmed COVID-19 infection incidence rate using Poisson regression with treatment group and age strata as fixed effects and robust error variance, where VE = 100 × (1 – ratio of incidence rate) (Zou 2004).

Descriptive analyses of efficacy showed efficacy point estimates similar to the estimate for the overall study population across genders and racial groups, and across participants with or without medical comorbidities associated with high risk of severe COVID-19. Vaccine efficacy in participants of Hispanic/Latino ethnicity was 77.4% (95% CI: 49.6%, 89.8%), and in participants who were not Hispanic/Latino, it was 93.2% (95% CI: 86.3%, 96.6%). Vaccine efficacy in participants 65 years of age and older was 68.0% (95% CI: -43.0%, 92.8%), and in participants 50 through 64 years of age, it was 89.2% (95% CI: 67.9%, 96.4%).

Immunogenicity of a Single Dose (Original Monovalent) in Vaccine-Experienced Adults

Effectiveness of a booster dose of Novavax COVID-19 Vaccine, Adjuvanted (Original monovalent) in vaccine-experienced adults was based on assessment of neutralizing antibody titers (MN50) against the original SARS-CoV-2 strain (SARS-CoV-2 hCoV-19/Australia/VIC01/2020). Immunogenicity analyses compared the MN50 titers following the booster dose to the MN50 titers following the primary series.

In the open-label booster dose phase of Study 1, participants 18 years of age and older received a single booster dose of Novavax COVID-19 Vaccine, Adjuvanted (Original monovalent) at least 6 months after completion of the primary series. A subset of 225 participants were included in the per-protocol immunogenicity (PP-IMM) analysis set. The median age of participants in the PP-IMM analysis set was 52 years (range 19 to 79 years). Overall, 52.0% were male and 48.0% were female; 82.7% were White, 9.3% were Black or African American, 0.4% were American Indian or Alaskan Native, 0.4% were Native Hawaiian or Other Pacific Islander, 5.8% were Asian, and 1.3% were Multiracial; 14.7% were Hispanic or Latino.

Prespecified noninferior immunogenicity analyses included an assessment of MN50 geometric mean titer (GMT) ratio and difference in seroconversion rates. Seroconversion for a participant was defined as achieving a 4-fold rise in MN50 from baseline (before the booster dose and before the first dose of the primary series).

The analysis of the GMT ratio of MN50 following the booster dose compared with that following the primary series met the noninferiority criteria for a booster dose response (lower limit of the 95% CI > 0.67) and point estimate > 0.83 (see Table 9).

Table 9: Neutralizing Antibody Geometric Titers (MN50) and Seroconversion Rates Against the Original SARS-CoV-2 Virus Strain (Ancestral Wuhan Strain) at 28 Days After a Booster Dose Versus 14 Days After Completion of the Primary Series, Participants ≥ 18 Years of Age, Study 1 PP-IMM Analysis Seta
Assay | Time Point | Booster Dose n=222b | Primary Series n=222b | GMR (95% CI)c | Met Noninferiority Criteriag,h
Assay | Time Point | GMT (95% CI)c | GMT (95% CI)c | GMR (95% CI)c | Met Noninferiority Criteriag,h
SARS-CoV-2 wild-type microneutralization assay (1/dilution) | 28 days after Booster Dose; 14 days after Primary Series Dose 2 | 4947.1 (4315.6, 5671.1) | 1553.4 (1277.3, 1889.1) | 3.2 (2.7, 3.8) | Yes
SARS-CoV-2 wild-type microneutralization assay (1/dilution) | 28 days after Booster Dose; 14 days after Primary Series Dose 2 | SCR n(%) (95% CI)d | SCR n(%) (95% CI)d | Difference in SCR%e (95% CI)f | Yes
SARS-CoV-2 wild-type microneutralization assay (1/dilution) | 28 days after Booster Dose; 14 days after Primary Series Dose 2 | 205 (92.3) (88.0, 95.5) | 209 (94.1) (90.2, 96.8) | -1.8 (-6.1, 2.3) | Yes
Abbreviations: CI = confidence interval; GMT = geometric mean titer; MN50 = microneutralization assay with an inhibitory concentration of 50%; PP-IMM = Per-Protocol Immunogenicity; SCR = seroconversion rate.
a PP-IMM Analysis Set included participants who received two doses (0.5 mL 21 days apart) of Novavax COVID-19 Vaccine, Adjuvanted (Original monovalent) in the initial vaccination period or in the blinded crossover vaccination period, had an immunogenicity blood sample collected at Day 35, did not have serologic or virologic evidence of SARS-CoV-2 infection up to 28 days post booster dose, did not receive an emergency use authorized COVID-19 vaccine, received the booster dose, and remained blinded on study and without major protocol deviations until 7 days post-crossover Dose.
b The analysis included a total of 222 participants of the PP-IMM analysis set who had immunogenicity data (microneutralization) available for both the booster dose and primary series.
c The 95% CI for GMT and GMT ratio were calculated based on the t-distribution of the log-transformed values, then back transformed to the original scale for presentation.
d The 95% CI for SCR was based on the Clopper-Pearson method.
e Comparison between SCR of 28 days post-booster dose relative to time of booster dose and SCR of 14 days after second dose of the primary series relative to time of first dose.
f Based on the Tango method.
g Noninferiority of the single booster dose was achieved if the lower limit of the 95% CI for the ratio of MN50 GMT at 28 days after a single booster dose versus 14 days after the second dose of NVX-CoV2373 was > 0.67 and the point estimate > 0.83.
h Noninferiority of the single booster dose was achieved if the lower limit of the 95% CI for the difference of the proportion of participants with SCR at 28 days after a single booster dose relative to the time of booster dose vaccination versus at 14 days after the second dose of Novavax COVID-19 Vaccine, Adjuvanted (Original monovalent) relative to the time of first vaccination was > -10%.
Note: The median duration between the time of the second dose of Novavax COVID-19 Vaccine, Adjuvanted (Original monovalent) and the time of the booster dose was 11 months.
Note: The SCR percentage was defined as percentage of participants at the post vaccination visit with a >= 4-fold rise from baseline if baseline is equal to or above LLOQ, or at least 4-fold rise from LLOQ if baseline is below LLOQ in antibody.

Immunogenicity of a Single Dose (Monovalent Omicron XBB.1.5) in Vaccine-Naïve Adults with Evidence of Prior SARS-CoV-2 Infection and in Vaccine-Experienced Adults

Study 7 was an open-label, single arm study conducted in the US and US territories that included participants 18 years of age and older. This study compared specific immune responses of COVID-19 vaccine-naïve participants who had a clinical history of COVID-19-like disease with immunologic or virologic evidence of prior SARS-CoV-2 infection (defined as a positive Roche Elecsys immunoassay result at Day 0) and no active infection (defined as a negative RT-PCR test at Day 0) with those of participants who were previously vaccinated (received at least 3 doses of the Pfizer-BioNTech COVID-19 Vaccine or the Moderna COVID-19 Vaccine). All participants received a single dose of Novavax COVID-19 Vaccine, Adjuvanted (2023-2024 Formula). The primary immunogenicity analysis population included 288 participants who were baseline SARS-CoV-2 seropositive and COVID-19 vaccine-naïve and 305 participants who were previously vaccinated. Among vaccine-naïve participants in the primary immunogenicity analysis subset, the median age of participants was 38 years, 40.6% were male, 59.4% were female; 50.0% were White, 43.1% were African American or Black, 2.1% were American Indian or Alaska Native, 0.7% were Asian, 0.3% were Native Hawaiian or Other Pacific Islander, 0.7% were other races, and 1.7% were Multiracial; 26.0% were Hispanic or Latino. Among participants who were previously vaccinated, the median age of participants was 53 years, 38.4% were male, 61.6% were female; 75.1% were White, 14.8% were African American or Black, 3.9% were Asian, 2.0% were American Indian or Alaska Native, 0.7% were Native Hawaiian or Other Pacific Islander, 0.3% were other races, and 1.0% were Multiracial; 19.7% were Hispanic or Latino.

The co-primary immunogenicity analyses of the GMT ratio and seroresponse rates (defined as the percentage of participants achieving a 4-fold rise in titer from baseline) against a pseudovirus expressing Omicron XBB.1.5 following the single dose in vaccine-naïve participants compared with after a single dose in participants who were previously vaccinated met the pre-defined success criteria for noninferiority for Omicron XBB.1.5. These analyses are summarized in Table 10.

Table 10: Geometric Mean Titers and Seroresponse Rates Against the XBB.1.5 SARS-CoV-2 Spike Protein at 28 Days After a Single Dose of Novavax COVID-19 Vaccine, Adjuvanted (2023-2024 Formula) in Vaccine-naïve Participants 18 Years of Age and Older and in Previously Vaccinated Participants 18 Years of Age and Older (Study 7, PP Pseudovirus Neutralization Assay Novavax Clinical Immunology Subset)
 | Vaccine-naïvea n=288 | Previously Vaccinatedb n=305
 | Vaccine-naïvea n=288 | Baseline GMT (95% CI) | 67.6 (56.8, 80.4) | 120.8 (101.5, 143.8)
Post-Vaccination Adjusted GMT (95% CI)c | 1491.5 (1277.5, 1741.4) | 841.4 (723.9, 978.0)
GMT Ratioc (95% CI) | 1.8d (1.4, 2.2)
SRRe % (95% CI) | 74.3 (68.9, 79.3) | 64.3 (58.6, 69.6)
Difference in SRR % (95% CI)f | 10.0g (2.6, 17.4)
Abbreviations: CI = confidence interval; GMT = geometric mean titer; n = number of participants in the assay-specific PP-IMM Analysis Set with non-missing data at both Baseline and Day 28 for this strain; LLOQ = lower limit of quantification; NP = nucleocapsid protein; PCR = polymerase chain reaction; PP = Per-Protocol; SARS-CoV-2 = severe acute respiratory syndrome coronavirus 2; SSR = seroresponse rate.
a The PP Pseudovirus Neutralization Assay Novavax Clinical Immunology Subset for vaccine-naïve participants included all participants with a clinical history of COVID-19-like disease who had not received any COVID-19 vaccine prior to enrollment in Study 7, received the full regimen of the study vaccine according to protocol, were anti-NP antibody seropositive at baseline, were RT-PCR negative for active SARS-COV-2 infection at baseline, had neutralization assay results available at baseline and at Day 28, and had no major protocol violations that were considered clinically relevant to impact immunogenicity response.
b The PP Pseudovirus Neutralization Assay Novavax Clinical Immunology Subset for previously vaccinated participants included all participants who received at least 3 doses of an mRNA COVID-19 vaccine prior to enrollment in Study 7, received the full regimen of the study vaccine according to protocol, were RT-PCR negative for active SARS-CoV-2 infection at baseline, had neutralization assay results available at baseline and at Day 28, and had no major protocol violations or an event that were considered clinically relevant to impact immunogenicity response.
c An ANCOVA with vaccine group as fixed effect and baseline value (Day 0) as covariate was performed to estimate the adjusted GMT and GMT ratio. The mean difference between vaccine groups and the corresponding CI limits was then exponentiated to obtain the ratio of GMTs and the corresponding 95% CIs.
d Noninferiority was met, as the lower bound of the two-sided 95% CI for the GMT ratio exceeded 0.67.
e The SRR percentage was defined as percentage of participants at the post vaccination visit with a ≥ 4-fold rise from baseline if baseline was equal to or above LLOQ, or at least 4-fold rise from LLOQ if baseline was below LLOQ in antibody. The 95% CI for SRR was calculated using the Clopper-Pearson exact method.
f Difference in SRR is the SRR in vaccine-naïve minus SRR in previously vaccinated. The 95% CI for the difference of SRR between groups was calculated with the method of Miettinen and Nurminen
g Noninferiority was met, as the lower bound of the two-sided 95% CI for the SRR difference was > -10%.

14.2 Adolescents 12 Years Through 17 Years of Age

Effectiveness of 2-Dose Series (Original Monovalent) in Vaccine-Naïve Adolescents

Effectiveness of a 2-dose series in adolescents 12 years through 17 years of age is based on a comparison of immune responses in this age group to adults 18 years through 25 years of age.

Study 1 adolescent expansion was a Phase 3 multicenter, randomized, observer-blinded, placebo-controlled, crossover study that included 2,247 participants 12 through 17 years of age at selected sites in the US from a diverse population including underserved minorities [see Adverse Reactions (6.1)]. Eligible participants were healthy or medically stable and had no history of previous laboratory-confirmed (by PCR or serology to SARS-CoV-2) diagnosis of SARS-CoV-2 infection or COVID-19 prior to randomization. SARS-CoV-2 PCR samples were tested by a central laboratory. The study excluded individuals who were significantly immunocompromised due to immunodeficiency disease; had received chronic immunosuppressive therapy or had received immunoglobulin or blood-derived products within 90 days; or had a history of laboratory-confirmed diagnosed COVID-19. Participants were enrolled without further stratification, although sites were instructed to recruit a similar number of participants in the 12 to < 15 years and 15 to < 18 years subgroups and randomized to Novavax COVID-19 Vaccine, Adjuvanted (Original monovalent) or placebo (normal saline) in a 2:1 ratio. A total of 2,247 participants were randomized to receive two doses of Novavax COVID-19 Vaccine, Adjuvanted (Original monovalent) or placebo 21 days apart. Assessments of safety, immunogenicity, and efficacy against COVID-19 were conducted for up to 24 months after the second dose.

The primary analysis was conducted comparing SARS-CoV-2 neutralizing antibody titers 14 days after Dose 2 in a subset of adolescents 12 through 17 years of age to those of participants 18 through 25 years of age from the adult main study. In the adolescent subset, the median age was 14 years; 52.4% were male and 47.6% were female; 79.8% were White, 11.2% were Black or African American, 1.1% were American Indian or Alaskan Native, 0.2% were Native Hawaiian or Other Pacific Islander, 2.4% were Asian, 5.2% were Multiracial, and 0.2% did not report a race; 17.2% were Hispanic or Latino. In the adult subset, the median age was 22 years; 46.7% were male and 53.3% were female; 69.7% were White, 10.4% were Black or African American, 8.7% were American Indian or Alaskan Native, 0.5% were Native Hawaiian or Other Pacific Islander, 7.3% were Asian, 1.7% were Multiracial, 1.5% did not report a race, and race information was missing for 0.2%; 32.4% were Hispanic or Latino.

Noninferior immune responses as assessed by geometric mean titers and seroconversion rates were demonstrated in a comparison of adolescents 12 through 17 years of age to participants 18 through 25 years of age (see Table 11).

Table 11: SARS-CoV-2 Neutralizing Antibody Geometric Mean Titer Ratio and Seroconversion Rate – Comparison of Adolescents 12 Years Through 17 Years of Age to Participants 18 Years Through 25 Years of Age, Study 1 – Per-Protocol Immunogenicity Analysis Set
Assay | Time Point | 12 Years Through 17 Years | 18 Years Through 25 Years | Analysis | Met Noninferiority Criteriac
Assay | Time Point | SARS-CoV-2 wild-type microneutralization assay (1/dilution)d | 14 days after Dose 2 | GMTa (95% CI) n=466 | GMTa (95% CI) n=413 | GMRb (95% CI) | Yes
3791.2 (3411.6, 4213.1) | 2603.3 (2359.1, 2872.9) | SARS-CoV-2 wild-type microneutralization assay (1/dilution)d | 14 days after Dose 2 | 1.5 (1.3, 1.7)c |  |  | Yes
SCR%e (95% CI) n=461 | SCR%e (95% CI) n=410 | SARS-CoV-2 wild-type microneutralization assay (1/dilution)d | 14 days after Dose 2 | Difference in SCR%f (95% CI) |  |  | Yes
98.9 (97.5, 99.7) | 99.3 (97.9, 99.8) | SARS-CoV-2 wild-type microneutralization assay (1/dilution)d | 14 days after Dose 2 | -0.3 (-1.9, 1.2) |  |  | Yes
CI = Confidence interval; GMR = Geometric mean ratio; GMT = Geometric mean titer; SCR = Seroconversion rate
a The 95% CI for GMT was calculated based on the t-distribution of the log-transformed values, then back transformed to the original scale for presentation.
b GMR is defined as the ratio of two geometric mean titers for comparison of two age cohorts. An analysis of covariance (ANCOVA) with age cohort as main effect and baseline microneutralization assay neutralizing antibodies as covariate was performed to estimate the GMR.
c Noninferiority was achieved if the following 3 pre-specified criteria were met simultaneously: 1) Upper limit of two-sided 95% CI for the ratio of GMTs (GMT12-17yo/GMT18-25yo) > 0.67; 2) Point estimate of the ratio of GMTs ≥ 0.82; and 3) Upper limit of the two-sided 95% CI for difference of SCRs (SCR12-17yo – SCR18-25yo) was > -10%.
d Validated virus neutralizing assay (VNA) with wild-type virus (SARS-CoV-2 hCoV-19/Australia/VIC01/2020 [GenBank MT007544.1]; 360biolabs, Melbourne, Australia). The lower limit for quantification for this assay was a titer of 20, with titers below this level documented as 10.
e The SCR percentage was defined as percentage of participants at the post vaccination visit with a >= 4-fold rise from baseline if baseline is equal to or above LLOQ, or at least 4-fold rise from LLOQ if baseline is below LLOQ in antibody. The 95% CI for SCR was calculated using the Clopper-Pearson exact method.
f Difference in SCR in the pediatric expansion minus the SCR in the adult part of the study for 18 through 25-year-old. The 95% CI for the difference of SCR between groups was calculated with the method of Miettinen and Nurminen.

A descriptive efficacy analysis evaluating PCR-confirmed symptomatic mild, moderate, or severe COVID-19 cases was performed prior to the crossover period in 1,788 participants who were included in the per-protocol efficacy (PP-EFF) Analysis Set.

Vaccine efficacy in participants without evidence of SARS-CoV-2 infection through 6 days after the second dose is presented in Table 12. The efficacy of Novavax COVID-19 Vaccine, Adjuvanted (Original monovalent) to prevent PCR-confirmed symptomatic mild, moderate, or severe COVID-19 from 7 days after Dose 2 was 79.8% (95% CI: 47.5%, 92.2%). All cases for which sequence data were available (vaccine n=3; placebo n=8) were due to the Delta variant. No cases of moderate or severe COVID-19 were reported in participants who received Novavax COVID-19 Vaccine, Adjuvanted (Original monovalent). One moderate and no severe cases of COVID-19 were reported in participants who received placebo.

Table 12: Vaccine Efficacy Against PCR-confirmed COVID-19 with Onset from 7 Days After Second Vaccinationa, Study 1 (PP-EFF Analysis Set)
Subgroup | Novavax COVID-19 Vaccine, Adjuvanted (Original Monovalent) |  |  | Placebo |  |  | Vaccine Efficacy (95% CI) (%)
Subgroup | Participants N | COVID-19 Cases n (%) | Mean Incidence Rate Per 100 Person-Years | Participants N | COVID-19 Cases n (%) | Mean Incidence Rate Per 100 Person-Years | Vaccine Efficacy (95% CI) (%)
Primary efficacy endpoint
All participants | 1,199 | 6 (0.5) | 2.9 | 590 | 14 (2.4) | 14.3 | 79.8 (47.5, 92.2)b
Mildc | – | 6 (0.5) | – | – | 13 (2.2) | – | –
Moderatec | – | 0 | – | – | 1 (0.2) | – | –
Severec | – | 0 | – | – | 0 | – | –
a Vaccine efficacy (VE) evaluated in participants without major protocol deviations who were seronegative (for SARS-CoV-2) at baseline and did not have a laboratory confirmed current SARS-CoV-2 infection with symptom onset through 6 days after the second dose, and who had received two doses of vaccine or placebo as randomized.
b Based on Modified Poisson regression with logarithmic link function and treatment group as fixed effect and robust error variance (Zou 2004).
c The definitions for mild, moderate, and severe COVID-19 disease used for the analysis of efficacy in adolescents 12 through 17 years of age were the same as those used for the assessment of efficacy in adults 18 years of age and older, with the exception of the inclusion of Multisystem Inflammatory Syndrome in Children (MIS-C) in the definition of severe COVID-19 disease for adolescents.

Immunogenicity of a Single Dose (Original Monovalent) in Vaccine-Experienced Adolescents

Effectiveness of a booster dose of Novavax COVID-19 Vaccine, Adjuvanted (Original monovalent) in vaccine-experienced adolescents was based on assessment of neutralizing antibody titers (MN50) against the original SARS-CoV-2 strain (SARS-CoV-2 hCoV-19/Australia/VIC01/2020). Immunogenicity analyses compared the MN50 titers following the booster dose with the MN50 titers following the primary series in participants who had data at both time points.

In the open-label booster dose phase of Study 1, participants 12 through 17 years of age received a single booster dose of Novavax COVID-19 Vaccine, Adjuvanted (Original monovalent) at least 5 months after completion of the primary series. A subset of 56 participants were included in the per-protocol immunogenicity (PP-IMM) analysis set. The median age of participants in the PP-IMM analysis set was 14 years (range 12 to 17 years). Overall, 51.8% were male and 48.2% were female; 91.1% were White, 1.8% were Black or African American, 1.8% were Asian, and 5.4% were Multiracial; 17.9% were Hispanic or Latino.

Prespecified analyses of noninferior immunogenicity included an assessment of MN50 GMT ratio and difference in seroconversion rates. Seroconversion for a participant was defined as achieving a 4-fold rise in MN50 from baseline (before the first dose of the primary series).

The analysis of the GMT ratio of MN50 following the booster dose compared with the primary series met the noninferiority criteria for a booster dose response (lower limit of the 95% CI > 0.67) and point estimate > 0.83.

The analysis of the difference in seroconversion rates following the booster dose compared with the pre-primary series met the noninferiority criteria for a booster dose response (lower limit of the 95% CI > -10%). These analyses are summarized in Table 13.

Table 13: Neutralizing Antibody Geometric Titers (MN50) and Seroconversion Rates Against the Original SARS-CoV-2 Virus Strain (Ancestral Wuhan Strain) at 28 Days After a Booster Dose Versus 14 Days After Completion of the Primary Series in Participants 12 Through 17 Years of Age, Study 1 PP-IMM Analysis Seta
Assay | Time Point | Booster Dose n=56b | Primary Series n=56b | GMR (95% CI)c | Met Noninferiority Criteriag,h
Assay | Time Point | GMT (95% CI)c | GMT (95% CI)c | GMR (95% CI)c | Met Noninferiority Criteriag,h
SARS-CoV-2 wild-type microneutralization assay (1/dilution) | 28 days after Booster Dose; 14 days after Primary Series Dose 2 | 12177.5 (9294.6, 15954.6) | 4305.4 (3543.7, 5230.7) | 2.8 (2.1, 3.8) | Yes
SARS-CoV-2 wild-type microneutralization assay (1/dilution) | 28 days after Booster Dose; 14 days after Primary Series Dose 2 | SCR% (95% CI)d | SCR% (95% CI)d | Difference in SCR%e (95% CI)f | Yes
SARS-CoV-2 wild-type microneutralization assay (1/dilution) | 28 days after Booster Dose; 14 days after Primary Series Dose 2 | 100.0 (93.6, 100.0) | 100.0 (93.6, 100.0) | 0.0 (-6.4, 6.4) | Yes
Abbreviations: CI = confidence interval; GMT = geometric mean titer; MN50 = microneutralization assay with an inhibitory concentration of 50%; PP-IMM = Per-Protocol Immunogenicity; SCR = seroconversion rate.
a The PP-IMM Analysis Set included participants who received two doses (0.5 mL 21 days apart) of Novavax COVID-19 Vaccine, Adjuvanted (Original monovalent) in the initial vaccination period , had an immunogenicity blood sample collected at Day 35 (primary series) and at 28 days after booster dose vaccination, did not have serologic or virologic evidence of SARS-CoV-2 infection on or before the booster dose, did not receive an emergency use authorized COVID-19 vaccine, received the booster dose, and remained blinded on study and without major protocol deviations until 7 days post-crossover Dose.
b The analysis included a total of 56 participants of the PP-IMM analysis set who had immunogenicity data available for both the booster dose and primary series.
c The 95% CI for GMT and GMT ratio were calculated based on the t-distribution of the log-transformed values, then back transformed to the original scale for presentation.
d The 95% CI for SCR was based on the Clopper-Pearson method.
e The difference in SCR was based on the Tango method.
f Comparison between SCR of 28 days post-booster dose relative to time of first dose and SCR of 14 days after second dose of the primary series relative to time of first dose.
g Noninferiority of the single booster dose was achieved if the lower limit of the 95% CI for the ratio of MN50 GMT at 28 days after a single booster dose versus 14 days after the second dose of Novavax COVID-19 Vaccine, Adjuvanted (Original monovalent) was > 0.67 and point estimate > 0.83.
h Noninferiority of the single booster dose was achieved if the lower limit of the 95% CI for the difference of the proportion of participants with SCR at 28 days after a single booster dose relative to the time of first vaccination versus at 14 days after the second dose of Novavax COVID-19 Vaccine, Adjuvanted (Original monovalent) relative to the time of first vaccination was > -10%.
Note: The median duration between the time of the second dose of Novavax COVID-19 Vaccine, Adjuvanted (Original monovalent), and the time of the booster dose was 10.6 months.
Note: SCR was defined as percentage of subjects with a ≥ 4-fold rise from baseline if the baseline value is equal to or above LLOQ, or at least 4-fold rise from LLOQ if the baseline value is below LLOQ in antibody concentration.

16 HOW SUPPLIED/STORAGE AND HANDLING

NUVAXOVID is supplied as a pre-filled syringe (NDC 80631-207-01) containing 1 dose of 0.5 mL. Ten pre-filled syringes are supplied in a carton (NDC 80631-207-10).

Store in the original carton to protect from light.

Store in a refrigerator at 2°C to 8°C (36°F to 46°F).

Do not freeze.

17 PATIENT COUNSELING INFORMATION

Advise the vaccine recipient or caregiver to read the FDA-approved patient labeling.

Inform the vaccine recipient or caregiver of the potential benefits and risks of vaccination with NUVAXOVID.

Instruct the vaccine recipient or caregiver to report any adverse events to their healthcare provider or to the Vaccine Adverse Event Reporting System at 1-800-822-7967 and http://www.vaers.hhs.gov.

There is a pregnancy exposure registry for NUVAXOVID. Encourage individuals exposed to NUVAXOVID around the time of conception or during pregnancy to register by visiting https://c-viper.pregistry.com/.

novavax

Manufactured for:
Novavax, Inc.
Gaithersburg, MD 20878

©2025 Novavax, Inc. All rights reserved.

NUVAXOVID is a trademark of Novavax, Inc.

US License No. 2349

Revised: 8/2025

INFORMATION FOR RECIPIENTS AND CAREGIVERS
NUVAXOVIDTM (Noo-VAX-o-vid)
(COVID-19 Vaccine, Adjuvanted)
(2025-2026 Formula)

This summary is not intended to take the place of talking with your healthcare provider. If you have questions or would like more information, please talk with your healthcare provider.

What is NUVAXOVID?
NUVAXOVID is a vaccine to protect against COVID-19.

NUVAXOVID is for people who are:

- 65 years of age and older, or
- 12 years through 64 years of age at high risk for severe COVID-19.

Vaccination with NUVAXOVID may not protect all people who receive the vaccine.

NUVAXOVID does not contain SARS-CoV-2, the virus that causes COVID-19. NUVAXOVID cannot give you or your child COVID-19.

Who should not get NUVAXOVID?
You or your child should not get NUVAXOVID if you or your child had:

- a severe allergic reaction after a previous dose of NUVAXOVID or Novavax COVID-19 Vaccine, Adjuvanted
- a severe allergic reaction to any ingredient of this vaccine (see What are the ingredients in NUVAXOVID?)

What should you tell your vaccination provider before you or your child gets NUVAXOVID?

Tell your vaccination provider about all of your or your child’s medical conditions, including if you or your child:

- have any allergies
- had a severe allergic reaction after receiving a previous dose of any COVID-19 vaccine
- have had myocarditis (inflammation of the heart muscle) or pericarditis (inflammation of the lining outside the heart)
- have a fever
- have a bleeding disorder or are on a blood thinner
- are immunocompromised or are on a medicine that affects your immune system
- are pregnant or plan to become pregnant
- are breastfeeding
- have received any other COVID-19 vaccine
- have ever fainted in association with an injection

How is NUVAXOVID given?
NUVAXOVID is given as an injection into the muscle.

What are the risks of NUVAXOVID?

There is a remote chance that NUVAXOVID could cause a severe allergic reaction. A severe allergic reaction would usually occur within a few minutes to 1 hour after getting a dose. For this reason, your vaccination provider may ask you or your child to stay at the place where you or your child received the vaccine for monitoring after vaccination. Signs of a severe allergic reaction can include:

- Difficulty breathing
- Swelling of your face and throat
- A fast heartbeat
- A bad rash all over your body
- Dizziness and weakness

Myocarditis (inflammation of the heart muscle) and pericarditis (inflammation of the lining outside the heart) have occurred in some people who have received NUVAXOVID or Novavax COVID-19 Vaccine, Adjuvanted. The chance of having this occur is very low. You should seek medical attention right away if you or your child have any of the following symptoms after receiving the vaccine:

- Chest pain
- Shortness of breath
- Feelings of having a fast-beating, fluttering, or pounding heart

Side effects that have been reported in clinical trials with NUVAXOVID include:

- Myocarditis (inflammation of the heart muscle)
- Pericarditis (inflammation of the lining outside the heart)
- Injection site reactions: pain/tenderness, swelling, redness and itching
- General side effects: fatigue or generally feeling unwell, muscle pain, headache, joint pain, nausea, vomiting, fever, chills
- Allergic reactions such as hives and swelling of the face
- Swollen lymph nodes

Side effects that have been reported in post-authorization use with NUVAXOVID include:

- Severe allergic reactions
- Myocarditis (inflammation of the heart muscle)
- Pericarditis (inflammation of the lining outside the heart)
- Paresthesia (unusual feeling in the skin such as tingling or a crawling feeling), hypoesthesia (decreased feeling or sensitivity, especially in the skin)

These may not be all the possible side effects of NUVAXOVID. Ask your healthcare provider about any side effects that concern you.
Report vaccine side effects to the FDA and the Centers for Disease Control and Prevention (CDC) Vaccine Adverse Event Reporting System (VAERS) at 1-800-822-7967 or https://vaers.hhs.gov/reportevent.html.
In addition, you can report side effects to Novavax, Inc., at www.Nuvaxovid.com or 1-844-NOVAVAX (1-844-668-2829).

What if you are pregnant or breastfeeding?
If you or your child are pregnant or breastfeeding, discuss your options with your healthcare provider.
There is a pregnancy exposure registry that monitors pregnancy outcomes in women exposed to NUVAXOVID during pregnancy. Women who are vaccinated with NUVAXOVID during pregnancy are encouraged to enroll in the registry by visiting https://c-viper.pregistry.com/.

What are the ingredients in NUVAXOVID?

NUVAXOVID contains a recombinant form of the SARS-CoV-2 spike protein produced from baculovirus-infected Sf9 insect cells (derived from the fall armyworm, which is an insect related to moths and butterflies) and Matrix-M® adjuvant containing saponins derived from the soapbark tree (Quillaja saponaria Molina).

Other ingredients include:

- cholesterol
- phosphatidylcholine
- potassium dihydrogen phosphate
- potassium chloride
- disodium hydrogen phosphate dihydrate
- sodium chloride
- disodium hydrogen phosphate heptahydrate
- sodium dihydrogen phosphate monohydrate
- polysorbate 80

NUVAXOVID may also contain small amounts of baculovirus and insect cell proteins, baculovirus and cellular DNA, lentil lectin, methyl-α-D-mannopyranoside, simethicone, pluronic F-68, Triton X-100, Tergitol, and DL-α-tocopherol.
NUVAXOVID does not contain preservatives.

This Information for Recipients and Caregivers may have been updated. For the most recent Information for Recipients and Caregivers, please visit https://dailymed.nlm.nih.gov/dailymed/.
If you have questions, talk to your healthcare provider.
novavax
Manufactured for:
Novavax, Inc.
Gaithersburg, MD 20878
©2025 Novavax, Inc. All rights reserved.
NUVAXOVID is a trademark of Novavax, Inc.
US License No. 2349

Revised: 8/2025

PRINCIPAL DISPLAY PANEL - NUVAXOVID 2025-2026 Formula - Carton

NDC 80631-207-10

novavax

COVID-19 Vaccine, Adjuvanted

NUVAXOVIDTM

2025-2026 Formula

For intramuscular use.

For 65 years of age and older

For people 12 through 64 years at high risk for severe COVID-19

10 single-dose pre-filled syringes

Each syringe contains 1 dose of 0.5 mL

Rx Only

PRINCIPAL DISPLAY PANEL - NUVAXOVID 2025-2026 Formula - Syringe Label

COVID-19 Vaccine, Adjuvanted

NUVAXOVIDTM

2025-2026 Formula